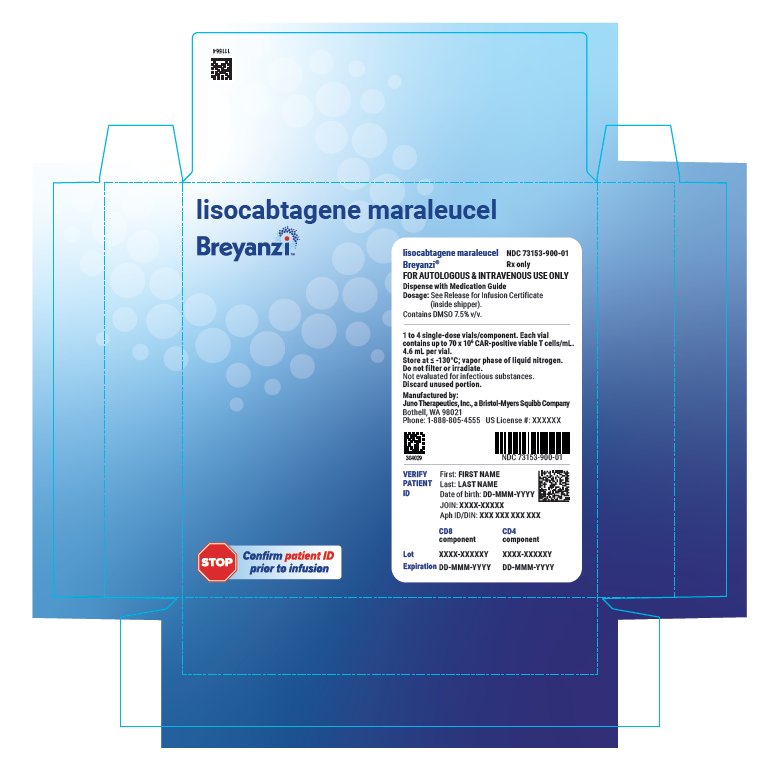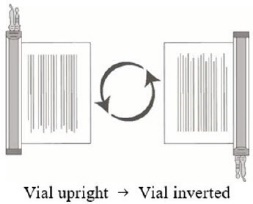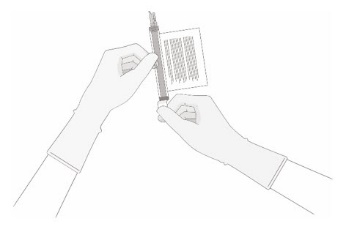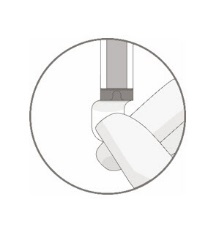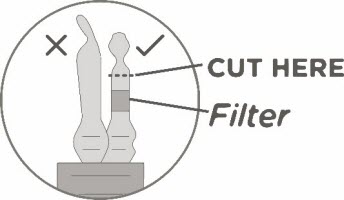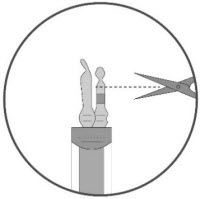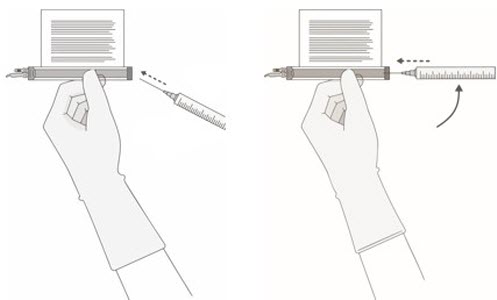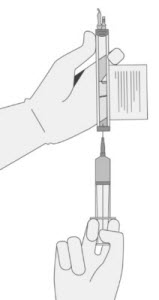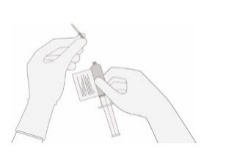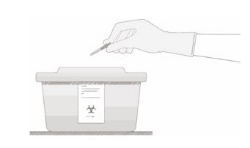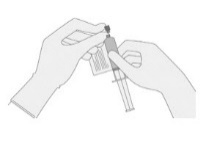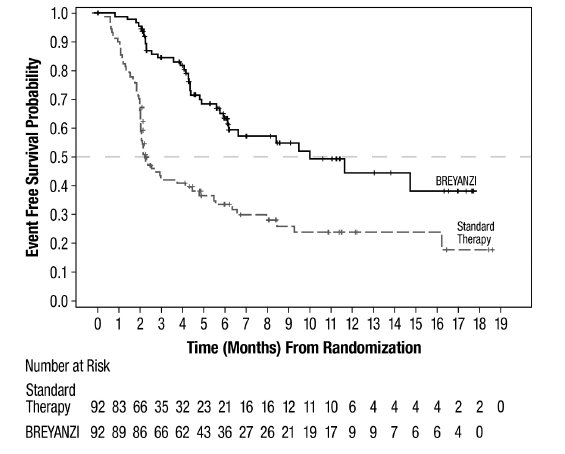 DRUG LABEL: BREYANZI
NDC: 73153-900 | Form: KIT | Route: INTRAVENOUS
Manufacturer: Juno Therapeutics, Inc.
Category: other | Type: CELLULAR THERAPY
Date: 20251204

ACTIVE INGREDIENTS: LISOCABTAGENE MARALEUCEL 50000000 1/5 mL; LISOCABTAGENE MARALEUCEL 50000000 1/5 mL
INACTIVE INGREDIENTS: DIMETHYL SULFOXIDE; ALBUMIN HUMAN; DIMETHYL SULFOXIDE; ALBUMIN HUMAN

HIGHLIGHTS OF PRESCRIBING INFORMATION

These highlights do not include all the information needed to use BREYANZI safely and effectively. See full prescribing information for BREYANZI.
BREYANZI® (lisocabtagene maraleucel) suspension for intravenous infusion
Initial U.S. Approval: 2021

RECENT MAJOR CHANGES

Indications and Usage, MZL (1.5) | 12/2025
Dosage and Administration (2.1) | 12/2025
Dosage and Administration (2.2, 2.3) | 6/2025
Warnings and Precautions, REMS Removed (5.3) | 6/2025
Warnings and Precautions (5.1, 5.2, 5.4, 5.6, 5.8) | 12/2025

WARNING: CYTOKINE RELEASE SYNDROME, NEUROLOGIC TOXICITIES, AND SECONDARY HEMATOLOGICAL MALIGNANCIES

See full prescribing information for complete boxed warning.

- Cytokine Release Syndrome (CRS), including fatal or life-threatening reactions, occurred in patients receiving BREYANZI. Do not administer BREYANZI to patients with active infection or inflammatory disorders. Treat severe or life-threatening CRS with tocilizumab with or without corticosteroids. (2.2, 2.3, 5.1)
- Neurologic toxicities, including fatal or life-threatening reactions, occurred in patients receiving BREYANZI, including concurrently with CRS, after CRS resolution, or in the absence of CRS. Monitor for neurologic events after treatment with BREYANZI. Provide supportive care and/or corticosteroids as needed. (2.2, 2.3, 5.2)
- T cell malignancies have occurred following treatment of hematologic malignancies with BCMA- and CD19-directed genetically modified autologous T cell immunotherapies, including BREYANZI. (5.7)

1 INDICATIONS AND USAGE

BREYANZI is a CD19-directed genetically modified autologous T cell immunotherapy indicated for the treatment of:

- adult patients with large B-cell lymphoma (LBCL), including diffuse large B-cell lymphoma (DLBCL) not otherwise specified (including DLBCL arising from indolent lymphoma), high-grade B-cell lymphoma, primary mediastinal large B-cell lymphoma, and follicular lymphoma grade 3B, who have:
  - refractory disease to first-line chemoimmunotherapy or relapse within 12 months of first-line chemoimmunotherapy; or
  - refractory disease to first-line chemoimmunotherapy or relapse after first-line chemoimmunotherapy and are not eligible for hematopoietic stem cell transplantation (HSCT) due to comorbidities or age; or
  - relapsed or refractory disease after 2 or more lines of systemic therapy. (1.1)

Limitations of Use: BREYANZI is not indicated for the treatment of patients with primary central nervous system lymphoma. (1, 14)

- adult patients with relapsed or refractory chronic lymphocytic leukemia (CLL) or small lymphocytic lymphoma (SLL) who have received at least 2 prior lines of therapy, including a Bruton tyrosine kinase (BTK) inhibitor and a B-cell lymphoma 2 (BCL-2) inhibitor. This indication is approved under accelerated approval based on response rate and duration of response. Continued approval for this indication may be contingent upon verification and description of clinical benefit in confirmatory trial(s). (1.2)
- adult patients with relapsed or refractory follicular lymphoma (FL) who have received 2 or more prior lines of systemic therapy. This indication is approved under accelerated approval based on response rate and duration of response. Continued approval for this indication may be contingent upon verification and description of clinical benefit in confirmatory trial(s). (1.3)
- adult patients with relapsed or refractory mantle cell lymphoma (MCL) who have received at least 2 prior lines of systemic therapy, including a Bruton tyrosine kinase (BTK) inhibitor. (1.4)
- adult patients with relapsed or refractory marginal zone lymphoma (MZL) who have received at least 2 prior lines of systemic therapy. (1.5)

2 DOSAGE AND ADMINISTRATION

For autologous use only. For intravenous use only.

- Do NOT use a leukodepleting filter. (2.2)
- Administer a lymphodepleting regimen of fludarabine and cyclophosphamide before infusion of BREYANZI. (2.2)
- Verify the patient’s identity prior to infusion. (2.2)
- Premedicate with acetaminophen and an H1 antihistamine. (2.2)
- Confirm availability of tocilizumab prior to infusion. (2.2, 5.1)
- Dosing of BREYANZI is based on the number of chimeric antigen receptor (CAR)-positive viable T cells. (2.1)
For LBCL:
- after one line of therapy, the dose is 90 to 110 × 10^6 CAR-positive viable T cells. (2.1)
- after two or more lines of therapy, the dose is 50 to 110 × 10^6 CAR-positive viable T cells. (2.1)
For CLL/SLL, FL, MCL and MZL:
- the dose is 90 to 110 × 10^6 CAR-positive viable T cells. (2.1)

3 DOSAGE FORMS AND STRENGTHS

- BREYANZI is a cell suspension for infusion. (3)
- A single dose of BREYANZI consists of 1:1 CAR-positive viable T cells of the CD8 and CD4 components, with each component supplied separately in one to four single-dose 5 mL vials. Each mL contains ≥ 1.5 × 10^6 to 70 × 10^6 CAR-positive viable T cells. (3)

4 CONTRAINDICATIONS

None. (4)

5 WARNINGS AND PRECAUTIONS

- Hypersensitivity Reactions: Monitor for hypersensitivity reactions during infusion. (5.3)
- Serious Infections: Monitor patients for signs and symptoms of infection; treat appropriately. (5.4)
- Prolonged Cytopenias: Patients may exhibit Grade 3 or higher cytopenias for several weeks following BREYANZI infusion. Monitor complete blood counts. (5.5)
- Hypogammaglobulinemia: Monitor and consider immunoglobulin replacement therapy. (5.6)
- Secondary Malignancies: T cell malignancies have occurred following treatment of hematologic malignancies with BCMA- and CD19-directed genetically modified autologous T cell immunotherapies, including BREYANZI. In the event that a secondary malignancy occurs after treatment with BREYANZI, contact Bristol-Myers Squibb at 1-888-805-4555. (5.7)

6 ADVERSE REACTIONS

The most common adverse reactions (incidence ≥ 30%) in:

- LBCL are fever, CRS, fatigue, musculoskeletal pain, and nausea. The most common Grade 3-4 laboratory abnormalities include lymphocyte count decrease, neutrophil count decrease, platelet count decrease, and hemoglobin decrease. (6.1)
- CLL/SLL are CRS, encephalopathy, fatigue, musculoskeletal pain, nausea, edema and diarrhea. The most common Grade 3-4 laboratory abnormalities include neutrophil count decrease, white blood cell decrease, hemoglobin decrease, platelet count decrease, and lymphocyte count decrease. (6.1)
- FL are CRS. The most common Grade 3-4 laboratory abnormalities include lymphocyte count decreased, neutrophil count decreased, and white blood cell decreased. (6.1)
- MCL are CRS, fatigue, musculoskeletal pain, and encephalopathy. The most common Grade 3-4 laboratory abnormalities include neutrophil count decrease, white blood cell decrease, and platelet count decrease. (6.1)
- MZL are CRS. The most common Grade 3-4 laboratory abnormalities include lymphocyte count decreased, neutrophil count decreased, and white blood cell decreased. (6.1)

To report SUSPECTED ADVERSE REACTIONS, contact Bristol-Myers Squibb at 1-800-721-5072 or FDA at 1-800-FDA-1088 or www.fda.gov/medwatch.

FULL PRESCRIBING INFORMATION

WARNING: CYTOKINE RELEASE SYNDROME, NEUROLOGIC TOXICITIES, AND SECONDARY HEMATOLOGICAL MALIGNANCIES

- Cytokine Release Syndrome (CRS), including fatal or life-threatening reactions, occurred in patients receiving BREYANZI. Do not administer BREYANZI to patients with active infection or inflammatory disorders. Treat severe or life-threatening CRS with tocilizumab with or without corticosteroids [see Dosage and Administration (2.2, 2.3) and Warnings and Precautions (5.1)].
- Neurologic toxicities, including fatal or life-threatening reactions, occurred in patients receiving BREYANZI, including concurrently with CRS, after CRS resolution, or in the absence of CRS. Monitor for neurologic events after treatment with BREYANZI. Provide supportive care and/or corticosteroids as needed [see Dosage and Administration (2.2, 2.3) and Warnings and Precautions (5.2)].
- T cell malignancies have occurred following treatment of hematologic malignancies with BCMA- and CD19-directed genetically modified autologous T cell immunotherapies, including BREYANZI [see Warnings and Precautions (5.7)].

1 INDICATIONS AND USAGE

1.1 Large B-cell Lymphoma (LBCL)

BREYANZI is indicated for the treatment of adult patients with large B-cell lymphoma (LBCL), including diffuse large B-cell lymphoma (DLBCL) not otherwise specified (including DLBCL arising from indolent lymphoma), high-grade B-cell lymphoma, primary mediastinal large B-cell lymphoma, and follicular lymphoma grade 3B who have:

- refractory disease to first-line chemoimmunotherapy or relapse within 12 months of first-line chemoimmunotherapy; or
- refractory disease to first-line chemoimmunotherapy or relapse after first-line chemoimmunotherapy and are not eligible for hematopoietic stem cell transplantation (HSCT) due to comorbidities or age; or
- relapsed or refractory disease after 2 or more lines of systemic therapy.

Limitations of Use: BREYANZI is not indicated for the treatment of patients with primary central nervous system (CNS) lymphoma [see Clinical Studies (14.1)].

1.2 Chronic Lymphocytic Leukemia (CLL) or Small Lymphocytic Lymphoma (SLL)

BREYANZI is indicated for the treatment of adult patients with relapsed or refractory chronic lymphocytic leukemia (CLL) or small lymphocytic lymphoma (SLL) who have received at least 2 prior lines of therapy including, a Bruton tyrosine kinase (BTK) inhibitor and a B-cell lymphoma 2 (BCL-2) inhibitor.

This indication is approved under accelerated approval based on response rate and duration of response [see Clinical Studies (14.2)]. Continued approval for this indication may be contingent upon verification and description of clinical benefit in confirmatory trial(s).

1.3 Follicular Lymphoma (FL)

BREYANZI is indicated for the treatment of adult patients with relapsed or refractory follicular lymphoma (FL) who have received 2 or more prior lines of systemic therapy.

This indication is approved under accelerated approval based on response rate and duration of response [see Clinical Studies (14.3)]. Continued approval for this indication may be contingent upon verification and description of clinical benefit in confirmatory trial(s).

1.4 Mantle Cell Lymphoma (MCL)

BREYANZI is indicated for the treatment of adult patients with relapsed or refractory mantle cell lymphoma (MCL) who have received at least 2 prior lines of systemic therapy, including a Bruton tyrosine kinase (BTK) inhibitor.

1.5 Marginal Zone Lymphoma (MZL)

BREYANZI is indicated for the treatment of adult patients with relapsed or refractory marginal zone lymphoma (MZL) who have received at least 2 prior lines of systemic therapy.

2 DOSAGE AND ADMINISTRATION

2.1 Dose

For autologous use only. For intravenous use only.

See the respective Certificate of Release for Infusion (RFI Certificate) for each component, for the actual cell counts and volumes to be infused [see Dosage and Administration (2.2) and Dosage Forms and Strengths (3)].

A single dose of BREYANZI contains CAR-positive viable T cells (consisting of 1:1 CAR-positive viable T cells of the CD8 and CD4 components), with each component supplied separately in one to four single-dose vials. See Table 1 for dose range per indication.

Table 1: Dose Range
Indication | BREYANZI dose range
LBCL after two or more lines of therapy (1.1) | 50 to 110 × 10^6 CAR-positive viable T cells
LBCL after one line of therapy (1.1) | 90 to 110 × 10^6 CAR-positive viable T cells
CLL or SLL (1.2) | 90 to 110 × 10^6 CAR-positive viable T cells
FL (1.3) | 90 to 110 × 10^6 CAR-positive viable T cells
MCL (1.4) | 90 to 110 × 10^6 CAR-positive viable T cells
MZL (1.5) | 90 to 110 × 10^6 CAR-positive viable T cells
Abbreviations: LBCL = large B-cell lymphoma; CLL = chronic lymphocytic leukemia; SLL = small lymphocytic lymphoma; FL = follicular lymphoma; MCL = mantle cell lymphoma; MZL = marginal zone lymphoma.

2.2 Administration

BREYANZI is for autologous use only. The patient’s identity must match the patient identifiers on the BREYANZI cartons, vials, and syringe labels. Do not infuse BREYANZI if the information on the patient-specific labels does not match the intended patient.

Preparing the Patient for BREYANZI

Confirm the availability of BREYANZI before starting lymphodepleting chemotherapy.

Pretreatment

Administer the lymphodepleting chemotherapy regimen before infusion of BREYANZI: fludarabine 30 mg/m^2/day intravenously (IV), and cyclophosphamide 300 mg/m^2/day IV for 3 days. See the prescribing information for fludarabine and cyclophosphamide for information on dose adjustment in renal impairment.

Infuse BREYANZI 2 to 7 days after completion of lymphodepleting chemotherapy.

Delay the infusion of BREYANZI if the patient has unresolved serious adverse events from preceding chemotherapies, active uncontrolled infection, or active graft-versus-host disease (GVHD).

Premedication

To minimize the risk of infusion reactions, premedicate the patient with acetaminophen (650 mg orally) and diphenhydramine (25-50 mg, IV or orally), or another H1-antihistamine, 30 to 60 minutes prior to treatment with BREYANZI.

Avoid prophylactic use of systemic corticosteroids, as they may interfere with the activity of BREYANZI.

Receipt of BREYANZI

- BREYANZI is shipped directly to the cell-associated lab or clinical pharmacy associated with the infusion center in the vapor phase of a liquid nitrogen shipper.
- Confirm the patient’s identity with the patient identifiers on the shipper.
- If the patient is not expected to be ready for administration before the shipper expires and the infusion site is qualified for onsite storage, transfer BREYANZI to onsite vapor phase of liquid nitrogen storage prior to preparation.
- If the patient is not expected to be ready for administration before the shipper expires and the infusion site is not qualified for onsite storage, contact Bristol-Myers Squibb at 1-888-805-4555 to arrange for return shipment.

Preparing BREYANZI

Before thawing the vials

- Confirm the patient’s identity with the patient identifiers on the RFI Certificate.
- Read the RFI Certificate (affixed inside the shipper) for information on the number of syringes you will need to administer the CD8 and CD4 components (syringe labels are provided with the RFI Certificate). There is a separate RFI Certificate for each cell component.
- Confirm tocilizumab and emergency equipment are available prior to infusion and during the recovery period.
- Confirm the infusion time in advance and adjust the start time of BREYANZI thaw such that it will be available for infusion when the patient is ready.

Thawing the vials

1. Confirm the patient’s identity with the patient identifiers on the outer carton and on the syringe labels.
  Once the vials of CAR-positive viable T cells (CD8 component and CD4 component) are removed from frozen storage, the thaw must be carried to completion and the cells administered within 2 hours.
2. Remove the CD8 component carton and CD4 component carton from the outer carton.
3. Confirm the patient’s identity with the patient identifiers on the inner carton.
4. Open each inner carton and visually inspect the vial(s) for damage. If the vials are damaged, contact Bristol-Myers Squibb at 1-888-805-4555.
5. Confirm the patient’s identity with the patient identifiers on the vials.
6. Carefully remove the vials from the cartons, place vials on a protective barrier pad, and thaw at room temperature until there is no visible ice in the vials. Thaw all of the vials at the same time. Keep the CD8 and CD4 components separate.

Dose preparation

- Prepare BREYANZI using sterile technique.
- Based on the concentration of CAR-positive viable T cells for each component, more than one vial of each of the CD8 and CD4 components may be required to complete a dose. A separate syringe should be prepared for each CD8 or CD4 component vial received.
  Note: The volume to be drawn up and infused may differ for each component as indicated on the RFI Certificate. Do NOT draw up excess volume into the syringe.
- Each vial contains 5 mL with a total extractable volume of 4.6 mL of CD8 or CD4 component T cells. The RFI Certificate for each component indicates the volume (mL) of cells to be drawn up into each syringe. Use the smallest Luer-lock tip syringe necessary (1, 3, or 5 mL) to draw up the specified volume from each vial. A 5 mL syringe should not be used for volumes less than 3 mL.
7. Prepare the syringe(s) of the CD8 component first. Affix the CD8 syringe labels to the syringe(s) prior to pulling the required volume into the syringe(s).
  Note: It is important to confirm that the volume drawn up for each component matches the volume specified in the respective RFI Certificate. Do NOT draw up excess volume into the syringe.

Withdrawal of the required volume of cells from each vial into a separate syringe should be carried out using the following instructions:

8. Hold the thawed vial(s) upright and gently invert the vial(s) 5 times to mix the cell product. If any clumping is apparent, continue to invert the vial(s) until clumps have dispersed and cells appear to be evenly resuspended.
9. Visually inspect the thawed vial(s) for damage or leaks. Do not use if the vial is damaged or if the clumps do not disperse; contact Bristol-Myers Squibb at 1-888-805-4555. The liquid in the vials should be slightly opaque to opaque, colorless to yellow or brownish-yellow.
10. Remove the polyaluminum cover (if present) from the bottom of the vial and swab the septum with an alcohol wipe. Allow to air dry before proceeding.
  Note: The absence of the polyaluminum cover does not impact the sterility of the vial.

11. Keeping the vial(s) upright, cut the seal on the tubing line on the top of the vial immediately above the filter to open the air vent on the vial.
  Note: Be careful to select the correct tubing line with the filter. Cut ONLY the tubing with a filter.

12. Hold a 20-gauge, 1-1 ½ inch needle, with the opening of the needle tip away from the retrieval port septum.
  a. Insert the needle into the septum at a 45°- 60° angle to puncture the retrieval port septum.
  b. Increase the angle of the needle gradually as the needle enters the vial.

a

b

13. WITHOUT drawing air into the syringe, slowly withdraw the target volume (as specified in the RFI Certificate). Carefully inspect the syringe for signs of debris prior to proceeding. If there is debris, contact Bristol-Myers Squibb at 1-888-805-4555.

14. Verify that the volume of CD8/CD4 component matches the volume specified for the relevant component in the RFI Certificate.
  Once the volume is verified, remove the syringe/needle from the vial, carefully detach the needle from the syringe and cap the syringe.

15. Continue to keep the vial horizontal and return it to the carton to avoid leaking from the vial.
16. Dispose of any unused portion of BREYANZI (according to local biosafety guidelines).
17. Repeat the process steps 7-16 for the CD4 Component.
18. Transport the labeled CD8 and CD4 syringes to the bedside by placing with protective barrier pad inside an insulated room temperature container.

BREYANZI Administration

- Do NOT use a leukodepleting filter.
- Confirm tocilizumab and emergency equipment are available prior to infusion and during the recovery period.
- Confirm the patient’s identity matches the patient identifiers on the syringe label.
- Once BREYANZI has been drawn into syringes, proceed with administration as soon as possible. The total time from removal from frozen storage to patient administration should not exceed 2 hours as indicated by the time entered on the syringe label.

19. Use intravenous normal saline to flush all the infusion tubing prior to and after each CD8 or CD4 component administration.

20. Administer the entire volume of the CD8 component intravenously at an infusion rate of approximately 0.5 mL/minute, using the closest port or Y-arm.
Note: The time for infusion will vary but will usually be less than 15 minutes for each component.

21. If more than one syringe is required for a full cell dose of the CD8 component, administer the volume in each syringe consecutively without any time between administering the contents of the syringes (unless there is a clinical reason (e.g., infusion reaction) to hold the dose).

22. After the CD8 component has been administered, flush the tubing with normal saline, using enough volume to clear the tubing and the length of the IV catheter.

23. Administer the CD4 component second, immediately after administration of the CD8 component is complete, using steps 1-4, as described for the CD8 component. Following administration of the CD4 component, flush the tubing with normal saline, using enough volume to clear the tubing and the length of the IV catheter.

BREYANZI contains human blood cells that are genetically modified with replication-incompetent, self-inactivating lentiviral vector. Follow universal precautions and local biosafety guidelines applicable for the handling and disposal, to avoid potential transmission of infectious diseases.

Monitoring

- Monitor patients daily for at least 7 days following BREYANZI infusion for signs and symptoms of CRS and neurologic toxicities.
- Instruct patients to remain within proximity of a healthcare facility for at least 2 weeks following infusion.
- Advise patients to avoid driving for at least 2 weeks following infusion.

2.3 Management of Severe Adverse Reactions

Cytokine Release Syndrome

Identify cytokine release syndrome (CRS) based on clinical presentation [see Warnings and Precautions (5.1)]. Evaluate for and treat other causes of fever, hypoxia, and hypotension. If CRS is suspected, manage according to the recommendations in Table 2. Physicians may also consider management per current practice guidelines.

Patients who experience Grade 2 or higher CRS (e.g., hypotension not responsive to fluids, or hypoxia requiring supplemental oxygenation) should be monitored with continuous cardiac telemetry and pulse oximetry. For patients experiencing severe CRS, consider performing an echocardiogram to assess cardiac function. For severe or life-threatening CRS, consider intensive-care supportive therapy.

If concurrent neurologic toxicity is suspected during CRS, administer:

- Corticosteroids according to the more aggressive intervention based on the CRS and neurologic toxicity grades in Tables 2 and 3
- Tocilizumab according to the CRS grade in Table 2
- Antiseizure medication according to the neurologic toxicity in Table 3

Table 2: CRS Grading and Management Guidance
CRS Gradea | Tocilizumab | Corticosteroidsb
Grade 1; Fever | If less than 72 hours after infusion, consider tocilizumab 8 mg/kg IV over 1 hour (not to exceed 800 mg).; If 72 hours or more after infusion, treat symptomatically. | If less than 72 hours after infusion, consider dexamethasone 10 mg IV every 24 hours.; If 72 hours or more after infusion, treat symptomatically.
Grade 2; Symptoms require and respond to moderate intervention.; Oxygen requirement less than 40% FiO2, or hypotension responsive to fluids or low dose of one vasopressor, or Grade 2 organ toxicity. | Administer tocilizumab 8 mg/kg IV over 1 hour (not to exceed 800 mg).; Repeat tocilizumab every 8 hours as needed if not responsive to intravenous fluids or increasing supplemental oxygen. Limit to a maximum of 3 doses in a 24-hour period; maximum total of 4 doses. | If less than 72 hours after infusion, administer dexamethasone 10 mg IV every 12‑24 hours.; If 72 hours or more after infusion, consider dexamethasone 10 mg IV every 12‑24 hours.
Grade 2; Symptoms require and respond to moderate intervention.; Oxygen requirement less than 40% FiO2, or hypotension responsive to fluids or low dose of one vasopressor, or Grade 2 organ toxicity. | If no improvement within 24 hours or rapid progression, repeat tocilizumab and escalate dose and frequency of dexamethasone (10‑20 mg IV every 6 to 12 hours).; If no improvement or continued rapid progression, maximize dexamethasone, switch to high-dose methylprednisolone 2 mg/kg if needed. After 2 doses of tocilizumab, consider alternative immunosuppressants. Do not exceed 3 doses tocilizumab in 24 hours, or 4 doses in total.
Grade 3; Symptoms require and respond to aggressive intervention.; Oxygen requirement greater than or equal to 40% FiO2, or hypotension requiring high-dose or multiple vasopressors, or Grade 3 organ toxicity, or Grade 4 transaminitis. | Per Grade 2. | Administer dexamethasone 10 mg IV every 12 hours.
Grade 3; Symptoms require and respond to aggressive intervention.; Oxygen requirement greater than or equal to 40% FiO2, or hypotension requiring high-dose or multiple vasopressors, or Grade 3 organ toxicity, or Grade 4 transaminitis. | If no improvement within 24 hours or rapid progression of CRS, repeat tocilizumab and escalate dose and frequency of dexamethasone (10-20 mg IV every 6 to 12 hours).; If no improvement or continued rapid progression, maximize dexamethasone, switch to high-dose methylprednisolone 2 mg/kg if needed. After 2 doses of tocilizumab, consider alternative immunosuppressants. Do not exceed 3 doses tocilizumab in 24 hours, or 4 doses in total.
Grade 4; Life-threatening symptoms.; Requirements for ventilator support or continuous veno‑venous hemodialysis (CVVHD) or Grade 4 organ toxicity (excluding transaminitis). | Per Grade 2. | Administer dexamethasone 20 mg IV every 6 hours.
Grade 4; Life-threatening symptoms.; Requirements for ventilator support or continuous veno‑venous hemodialysis (CVVHD) or Grade 4 organ toxicity (excluding transaminitis). | If no improvement within 24 hours or rapid progression of CRS, escalate tocilizumab and corticosteroid use. If no improvement or continued rapid progression, maximize dexamethasone, switch to high-dose methylprednisolone 2 mg/kg if needed. After 2 doses of tocilizumab, consider alternative immunosuppressants. Do not exceed 3 doses tocilizumab in 24 hours, or 4 doses in total.
a Lee criteria for grading CRS (Lee et al, 2014).
b If corticosteroids are initiated, continue corticosteroids for at least 3 doses or until complete resolution of symptoms, and consider corticosteroid taper.

Neurologic Toxicity

Monitor patients for signs and symptoms of neurologic toxicities (Table 3). Rule out other causes of neurologic symptoms. Provide intensive care supportive therapy for severe or life-threatening neurologic toxicities. If neurologic toxicity is suspected, manage according to the recommendations in Table 3. Physicians may also consider management per current practice guidelines.

If concurrent CRS is suspected during neurologic toxicity, administer:

- Corticosteroids according to the more aggressive intervention based on the CRS and neurologic toxicity grades in Tables 2 and 3
- Tocilizumab according to the CRS grade in Table 2
- Antiseizure medication according to the neurologic toxicity in Table 3

Table 3: Neurologic Toxicity (NT) Grading and Management Guidance
NT Gradea | Corticosteroids and Antiseizure Medication
Grade 1 | Start non-sedating, antiseizure medicines (e.g., levetiracetam) for seizure prophylaxis. If 72 hours or more after infusion, observe. If less than 72 hours after infusion, consider dexamethasone 10 mg IV every 12 to 24 hours for 2 to 3 days.
Grade 2 | Start non-sedating, antiseizure medicines (e.g., levetiracetam) for seizure prophylaxis. Dexamethasone 10 mg IV every 12 hours for 2-3 days, or longer for persistent symptoms. Consider taper for a total steroid exposure of greater than 3 days. If no improvement after 24 hours or worsening of neurologic toxicity, increase the dose and/or frequency of dexamethasone up to a maximum of 20 mg IV every 6 hours. If no improvement after another 24 hours, rapidly progressing symptoms, or life-threatening complications arise, give methylprednisolone (2 mg/kg loading dose, followed by 2 mg/kg divided 4 times a day; taper within 7 days).
Grade 3 | Start non-sedating, antiseizure medicines (e.g., levetiracetam) for seizure prophylaxis. Dexamethasone 10 to 20 mg IV every 8 to 12 hours. Steroids are not recommended for isolated Grade 3 headaches. If no improvement after 24 hours or worsening of neurologic toxicity, escalate to methylprednisolone (dose and frequency as per Grade 2). If cerebral edema is suspected, consider hyperventilation and hyperosmolar therapy. Give high-dose methylprednisolone (1-2 g, repeat every 24 hours if needed; taper as clinically indicated) and cyclophosphamide 1.5 g/m^2.
Grade 4 | Start non-sedating, antiseizure medicines (e.g., levetiracetam) for seizure prophylaxis. Dexamethasone 20 mg IV every 6 hours. If no improvement after 24 hours or worsening of neurologic toxicity, escalate to methylprednisolone (dose and frequency as per Grade 2). If cerebral edema is suspected, consider hyperventilation and hyperosmolar therapy. Give high-dose methylprednisolone (1-2 g, repeat every 24 hours if needed; taper as clinically indicated), and cyclophosphamide 1.5 g/m^2.
a NCI CTCAE criteria for grading neurologic toxicities, version 4.03.

3 DOSAGE FORMS AND STRENGTHS

BREYANZI is a cell suspension for infusion.

A single dose of BREYANZI contains CAR-positive viable T cells that consist of CD8 and CD4 components, with each component supplied separately in single-dose vials [see Dosage and Administration (2.1)].

More than one vial of each of the CD8 component and/or CD4 component may be needed to achieve the dose of BREYANZI.

Each vial contains between 6.9 × 10^6 and 322 × 10^6 CAR-positive viable T cells in 4.6 mL cell suspension (between 1.5 × 10^6 and 70 x 10^6 CAR-positive viable T cells/mL).

The infusion volume is calculated based on the concentration of cryopreserved drug product CAR-positive viable T cells. The volume may differ for each component infused. See the RFI Certificate for details [see How Supplied/Storage and Handling (16)].

4 CONTRAINDICATIONS

None.

5 WARNINGS AND PRECAUTIONS

5.1 Cytokine Release Syndrome

Cytokine release syndrome (CRS), including fatal or life-threatening reactions, occurred following treatment with BREYANZI.

In clinical trials of BREYANZI, which included a total of 769 patients with non-Hodgkin lymphoma (NHL) exposed to BREYANZI, CRS occurred in 56% of patients, including ≥ Grade 3 CRS (Lee grading system^1) in 3.4% of patients. The median time to onset was 5 days (range: 1 to 63 days). CRS resolved in 99% of patients with a median duration of 5 days (range: 1 to 37 days). One patient had fatal CRS and 5 patients had ongoing CRS at the time of death. The most common manifestations of CRS (≥ 10%) included fever, hypotension, chills, tachycardia, hypoxia, and headache.

Serious events that may be associated with CRS include cardiac arrhythmias (including atrial fibrillation and ventricular tachycardia), cardiac arrest, cardiac failure, diffuse alveolar damage, renal insufficiency, capillary leak syndrome, hypotension, hypoxia, and hemophagocytic lymphohistiocytosis/macrophage activation syndrome (HLH/MAS) [see Adverse Reactions (6.1)].

Ensure that 2 doses of tocilizumab are available prior to infusion of BREYANZI.

Monitor patients daily for at least 7 days following BREYANZI infusion for signs and symptoms of CRS. Continue to monitor patients for signs or symptoms of CRS for at least 2 weeks after infusion. At the first sign of CRS, institute treatment with supportive care, tocilizumab, or tocilizumab and corticosteroids as indicated [see Dosage and Administration (2.2, 2.3)].

Counsel patients to seek immediate medical attention should signs or symptoms of CRS occur at any time [see Patient Counseling Information (17)].

5.2 Neurologic Toxicities

Neurologic toxicities that were fatal or life-threatening, including immune effector cell-associated neurotoxicity syndrome (ICANS), occurred following treatment with BREYANZI. Serious events including cerebral edema and seizures occurred with BREYANZI. Fatal and serious cases of leukoencephalopathy, some attributable to fludarabine, also occurred.

In clinical trials of BREYANZI, CAR T cell-associated neurologic toxicities occurred in 32% of patients, including ≥ Grade 3 cases in 10% of patients. The median time to onset of neurotoxicity was 8 days (range: 1 to 63 days). Neurologic toxicities resolved in 88% of patients with a median duration of 7.5 days (range: 1 to 119 days). Of patients developing neurotoxicity, 83% also developed CRS.

The most common neurologic toxicities (≥ 5%) included encephalopathy, tremor, aphasia, delirium, and headache.

Monitor patients daily for at least 7 days following BREYANZI infusion for signs and symptoms of neurologic toxicities and assess for other causes of neurological symptoms. Continue to monitor patients for signs or symptoms of neurologic toxicities for at least 2 weeks after infusion and treat promptly. Manage neurologic toxicity with supportive care and/or corticosteroid as needed [see Dosage and Administration (2.2, 2.3)]. Advise patients to avoid driving for at least 2 weeks following infusion.

Counsel patients to seek immediate medical attention should signs or symptoms of neurologic toxicity occur at any time [see Patient Counseling Information (17)].

5.3 Hypersensitivity Reactions

Allergic reactions may occur with the infusion of BREYANZI. Serious hypersensitivity reactions, including anaphylaxis, may be due to dimethyl sulfoxide (DMSO).

5.4 Serious Infections

Severe infections, including life-threatening or fatal infections, have occurred in patients after BREYANZI infusion.

In clinical trials of BREYANZI, infections of any grade occurred in 33% of patients, with Grade 3 or higher infections occurred in 12% of all patients. Grade 3 or higher infections with an unspecified pathogen occurred in 7%, bacterial infections in 3.5%, viral infections in 2%, and fungal infections in 0.7% of patients. One patient with FL, who received four prior lines of therapy developed a fatal case of John Cunningham (JC) virus progressive multifocal leukoencephalopathy four months after treatment with BREYANZI. One patient with MCL, who received three prior lines of therapy, developed a fatal case of cryptococcal meningoencephalitis 35 days after treatment with BREYANZI.

Febrile neutropenia developed after BREYANZI infusion in 8% of patients. Febrile neutropenia may be concurrent with CRS. In the event of febrile neutropenia, evaluate for infection and manage with broad‑spectrum antibiotics, fluids, and other supportive care as medically indicated.

Monitor patients for signs and symptoms of infection before and after BREYANZI administration and treat appropriately. Administer prophylactic antimicrobials according to standard institutional guidelines.

Avoid administration of BREYANZI in patients with clinically significant, active systemic infections.

Viral Reactivation

Hepatitis B virus (HBV) reactivation, in some cases resulting in fulminant hepatitis, hepatic failure, and death, can occur in patients treated with drugs directed against B cells.

In clinical trials of BREYANZI, 35 of 38 patients with a prior history of HBV were treated with concurrent antiviral suppressive therapy. Perform screening for HBV, HCV, and HIV in accordance with clinical guidelines before collection of cells for manufacturing. In patients with prior history of HBV, consider concurrent antiviral suppressive therapy to prevent HBV reactivation per standard guidelines.

5.5 Prolonged Cytopenias

Patients may exhibit cytopenias not resolved for several weeks following lymphodepleting chemotherapy and BREYANZI infusion.

In clinical trials of BREYANZI, Grade 3 or higher cytopenias persisted at Day 29 following BREYANZI infusion in 35% of patients, and included thrombocytopenia in 25%, neutropenia in 22%, and anemia in 6% of patients.

Monitor complete blood counts prior to and after BREYANZI administration.

5.6 Hypogammaglobulinemia

B-cell aplasia and hypogammaglobulinemia can occur in patients receiving BREYANZI.

In clinical trials of BREYANZI, hypogammaglobulinemia was reported as an adverse reaction in 9% of patients. Hypogammaglobulinemia, either as an adverse reaction or laboratory IgG level below 500 mg/dL after infusion, was reported in 30% of patients.

Monitor immunoglobulin levels after treatment with BREYANZI and manage using infection precautions, antibiotic prophylaxis, and immunoglobulin replacement as clinically indicated.

Live Vaccines

The safety of immunization with live viral vaccines during or following BREYANZI treatment has not been studied. Vaccination with live virus vaccines is not recommended for at least 6 weeks prior to the start of lymphodepleting chemotherapy, during BREYANZI treatment, and until immune recovery following treatment with BREYANZI.

5.7 Secondary Malignancies

Patients treated with BREYANZI may develop secondary malignancies. T cell malignancies have occurred following treatment of hematologic malignancies with BCMA- and CD19-directed genetically modified autologous T cell immunotherapies, including BREYANZI. Mature T cell malignancies, including CAR-positive tumors, may present as soon as weeks following infusion, and may include fatal outcomes [see Boxed Warning, Adverse Reactions (6.2), Patient Counseling Information (17)]. Monitor lifelong for secondary malignancies. In the event that a secondary malignancy occurs, contact Bristol-Myers Squibb at 1-888-805-4555 for reporting and to obtain instructions on collection of patient samples for testing.

5.8 Immune Effector Cell-Associated Hemophagocytic Lymphohistiocytosis-Like Syndrome (IEC-HS)

Immune Effector Cell-Associated Hemophagocytic Lymphohistiocytosis-Like Syndrome (IEC-HS), including fatal or life-threatening reactions, occurred following treatment with BREYANZI. Seven out of 769 (0.9%) patients with R/R NHL exposed to BREYANZI developed IEC-HS (1 LBCL; 3 CLL/SLL; 3 MZL). Time to onset of IEC-HS ranged from 7 to 32 days. Of the 7 patients, 3 patients developed IEC-HS with overlapping occurrence of CRS and neurotoxicity, 2 patients developed IEC-HS with overlapping occurrence of neurotoxicity, and 1 patient developed IEC-HS with overlapping occurrence of CRS. IEC-HS was fatal in 2 of 7 patients. One patient had fatal IEC-HS and one had ongoing IEC-HS at time of death.

IEC-HS is a life-threatening condition with a high mortality rate if not recognized and treated early. Treatment of IEC-HS should be administered per current practice guidelines.

6 ADVERSE REACTIONS

6.1 Clinical Trials Experience

Because clinical trials are conducted under widely varying conditions, adverse reaction rates observed in the clinical trials of a drug cannot be directly compared to rates in the clinical trials of another drug and may not reflect the rates observed in practice.

The safety data described in the WARNINGS and PRECAUTIONS and in this section reflects exposure to a single dose of BREYANZI in 769 patients in five clinical studies as described below.

Study 1 (JCAR017-BCM-003; Relapsed or Refractory LBCL After One Line of Therapy)

Study 1 was a randomized, open-label, multicenter study, in which patients with primary refractory LBCL or relapse within 1 year of first-line chemoimmunotherapy received BREYANZI (N=89) or standard therapy (N=91) [see Clinical Studies (14.1)]. Patients had not yet received treatment for relapsed or refractory lymphoma and were potential candidates for autologous HSCT. The trial excluded patients who were ineligible for transplant or who had age > 75 years, Eastern Cooperative Oncology Group (ECOG) performance status >1, history of central nervous system (CNS) disorders (such as seizures or cerebrovascular ischemia), uncontrolled infection, CrCl < 45 mL/min, alanine aminotransferase (ALT) > 5 times the upper limit of normal (ULN), left ventricular ejection fraction (LVEF) < 40%, or absolute neutrophil count (ANC) < 1.0 × 10^9 cells/L or platelets < 50 × 10^9 cells/L in the absence of bone marrow involvement.

The planned dose of BREYANZI was 100 × 10^6 CAR-positive viable T cells. The median age of the BREYANZI-treated population was 59 years (range: 20 to 74 years); 47% were male; 58% were White, 11% were Asian, and 5% were Black.

Serious adverse reactions occurred in 38% of patients. The most common nonlaboratory serious adverse reactions (> 2%) were CRS, sepsis, fever, febrile neutropenia, headache, aphasia, COVID-19 infection, and pulmonary embolism.

Table 4 presents selected nonlaboratory adverse reactions in patients treated with BREYANZI, and Table 5 describes selected new or worsening Grade 3 or 4 laboratory abnormalities.

The most common nonlaboratory adverse reactions (≥ 20%) were fever, CRS, musculoskeletal pain, headache, fatigue, nausea, constipation, and dizziness.

Table 4: Adverse Reactions in ≥ 10% of Patients with Relapsed or Refractory LBCL Treated with BREYANZI in Study 1 (N=89)
Adverse Reaction | Any Grade (%) | Grade 3 or Higher (%)
Blood and lymphatic system disorders
Febrile neutropenia | 10 | 10
Cardiac disorders
Tachycardia* | 15 | 1.1
Gastrointestinal disorders
Nausea | 24 | 0
Constipation | 20 | 2.2
Diarrhea | 18 | 0
Abdominal pain* | 13 | 2.2
Vomiting | 11 | 0
General disorders and administration site conditions
Fever | 55 | 3.4
Fatigue* | 28 | 1.1
Edemaa | 13 | 0
Immune system disorders
Cytokine release syndrome | 49 | 1.1
Infections and infestations
Bacterial infectious disorders* | 12 | 6
Infections with pathogen unspecified* | 12 | 6
Sepsis* | 10 | 7
Metabolism and nutrition disorders
Decreased appetite | 15 | 0
Musculoskeletal and connective tissue disorders
Musculoskeletal pain* | 36 | 3.4
Nervous system disorders
Headache* | 34 | 6
Dizzinessb | 20 | 1.1
Motor dysfunctionc | 12 | 3.4
Tremord | 11 | 1.1
Psychiatric disorders
Insomnia* | 15 | 0
Respiratory, thoracic, and mediastinal disorders
Cough* | 11 | 0
Skin and subcutaneous tissue disorders
Rashe | 12 | 1.1
Vascular disorders
Hypotension* | 15 | 2.2
Hemorrhagef | 12 | 0
* Represents multiple related terms.
a Edema includes edema peripheral, localized edema, pleural effusion swelling.
b Dizziness includes dizziness, dizziness postural, syncope, vertigo.
c Motor dysfunction includes fine motor skill dysfunction, muscle spasms, muscular weakness.
d Tremor includes resting tremor, tremor, essential tremor.
e Rash includes catheter site rash, dermatitis acneiform, dermatitis exfoliative generalized, erythema multiforme, rash, rash maculo-papular, rash pruritic.
f Hemorrhage includes conjunctival hemorrhage, cystitis hemorrhagic, epistaxis, gastrointestinal hemorrhage, hematoma, hematuria, retinal hemorrhage, vaginal hemorrhage.

Other clinically important adverse reactions in < 10% of patients treated with BREYANZI included the following:

- Immune system disorders: Hemophagocytic lymphohistiocytosis (1.1%)
- Infections and infestations: Viral infection (9%), fungal infection (4.5%), pneumonia (2.2%)
- Nervous system disorders: Encephalopathy (8%), aphasia (4.5%), peripheral neuropathy (4.5%), ataxia (3.4%), paresis (1.1%)
- Psychiatric disorders: Delirium (2.2%)
- Renal and urinary disorders: Renal failure (3.4%)
- Respiratory, thoracic, and mediastinal disorders: Dyspnea (8%)
- Vascular disorders: Thrombosis (8%), hypertension (7%)

Table 5: Grade 3 or 4 Laboratory Abnormalities Occurring in ≥ 10% of Patients with Relapsed or Refractory LBCL Treated with BREYANZI in Study 1
Laboratory Abnormalitya | Grade 3 or 4 (%)b
Lymphocyte count decreased | 98
Neutrophil count decreased | 89
Platelet count decreased | 48
Hemoglobin decreased | 32
a Baseline lab values were assessed prior to lymphodepleting chemotherapy.
b Based on 88 evaluable patients, defined as those with both a baseline grade and at least one post-baseline grade for the particular lab.

Grade 4 laboratory abnormalities in ≥ 10% of patients were lymphocyte decrease (64%), neutrophil decrease (66%), and platelet decrease (34%).

Study 2 (017006; Relapsed or Refractory LBCL After One Line of Therapy)

Study 2 was a single-arm open-label study in transplant-ineligible patients with R/R LBCL after one line of chemoimmunotherapy [see Clinical Studies (14.1)]. The study enrolled patients who were ineligible for high-dose therapy and autologous HSCT due to organ function or age, but who had adequate organ function for CAR-T cell therapy. Patients with a history of relevant CNS disorders (such as seizures or cerebrovascular ischemia), ECOG performance status > 2, or uncontrolled infection were ineligible. The trial required LVEF ≥ 40%, adequate oxygen saturation on room air with ≤ Grade 1 dyspnea, AST, and ALT ≤ 5 x ULN, total bilirubin < 2.0 mg/dL, creatinine clearance > 30 mL/min, and adequate bone marrow function to receive lymphodepleting chemotherapy. The planned dose of BREYANZI was 100 × 10^6 CAR-positive viable T cells.

The median age was 74 years (range: 53 to 84 years), 90% were age ≥ 65 years, 61% were male. The ECOG performance status was 0 or 1 in 74% of patients and 2 in 26% of patients; 25% had CrCl < 60 ml/min; 20% had a baseline ANC < 1000/μL.

Serious adverse reactions occurred in 33% of patients. The most common nonlaboratory, serious adverse reactions (> 2%) were CRS, confusional state, gastrointestinal hemorrhage, muscular weakness, musculoskeletal pain, pulmonary embolism, and sepsis.

Table 6 presents selected nonlaboratory adverse reactions, and Table 7 describes selected new or worsening Grade 3 or 4 laboratory abnormalities.

The most common nonlaboratory adverse reactions (≥ 20%) were fatigue, CRS, fever, nausea, encephalopathy, hypotension, musculoskeletal pain, and edema.

Table 6: Adverse Reactions in ≥ 10% of Patients with Relapsed or Refractory LBCL Treated with BREYANZI in Study 2 (N=61)
Adverse Reaction | Any Grade (%) | Grade 3 or Higher (%)
Cardiac disorders
Tachycardia* | 10 | 0
Gastrointestinal disorders
Nausea | 25 | 1.6
Diarrhea | 15 | 0
Constipation | 11 | 0
General disorders and administration site conditions
Fatigue* | 44 | 1.6
Fever | 38 | 1.6
Edema* | 20 | 0
Immune system disorders
Cytokine release syndrome | 39 | 1.6
Infections and infestations
Infections with pathogen unspecified* | 13 | 4.9
Upper respiratory tract infection* | 13 | 0
Bacterial infectious disorders* | 10 | 3.3
Metabolism and nutrition disorders
Decreased appetite | 13 | 1.6
Musculoskeletal and connective tissue disorders
Musculoskeletal pain* | 23 | 4.9
Nervous system disorders
Encephalopathya | 23 | 4.9
Dizzinessb | 16 | 1.6
Tremorc | 16 | 0
Headache | 11 | 1.6
Psychiatric disorders
Insomnia | 11 | 0
Respiratory, thoracic, and mediastinal disorders
Cough* | 18 | 0
Dyspnea* | 16 | 4.9
Vascular disorders
Hypotension* | 23 | 1.6
Hypertension | 10 | 4.9
* Represents multiple related terms.
a Encephalopathy includes amnesia, apraxia, cognitive disorder, confusional state, depressed level of consciousness, disturbance in attention, dyscalculia, encephalopathy, lethargy, memory impairment, mental status changes, somnolence.
b Dizziness includes dizziness, dizziness postural, syncope, vertigo.
c Tremor includes resting tremor, tremor.

Other clinically important adverse reactions in < 10% of patients included the following:

- Blood and lymphatic system disorders: Febrile neutropenia (1.6%)
- Eye disorders: Vision blurred (3.3%)
- Gastrointestinal disorders: Vomiting (8%), abdominal pain (7%), gastrointestinal hemorrhage (4.9%)
- Infections and infestations: Fungal infection (4.9%), sepsis (3.3%), viral infection (3.3%)
- Nervous system disorders: Motor dysfunction (7%), aphasia (4.9%), ataxia (4.9%), peripheral neuropathy (4.9%)
- Psychiatric disorders: Delirium (3.3%)
- Renal and urinary disorders: Renal failure (7%)
- Respiratory, thoracic, and mediastinal disorders: Hypoxia (4.9%)
- Skin and subcutaneous tissue disorders: Rash (7%)
- Vascular disorders: Thrombosis (7%)

Table 7: Grade 3 or 4 Laboratory Abnormalities Occurring in ≥ 10% of Patients with Relapsed or Refractory LBCL Treated with BREYANZI in Study 2 (N=61)
Laboratory Abnormalitya | Grade 3 or 4 (%)
Lymphocyte count decreased | 97
Neutrophil count decreased | 80
Hemoglobin decreased | 30
Platelet count decreased | 26
a Baseline lab values were assessed prior to lymphodepleting chemotherapy.

Grade 4 laboratory abnormalities in ≥ 10% of patients were lymphocyte decrease (95%), neutrophil decrease (57%), and platelet decrease (20%).

Study 3 (017001; Relapsed or Refractory LBCL After Two or More Lines of Therapy)

Study 3 was an open-label, single-arm study which evaluated 268 adult patients with R/R LBCL after 2 or more prior lines of therapy received a single dose of CAR-positive viable T cells [see Clinical Studies (14.1)]. Patients with a history of CNS disorders (such as seizures or cerebrovascular ischemia) or autoimmune disease requiring systemic immunosuppression were ineligible. The median age of the study population was 63 years (range: 18 to 86 years); 65% were male. The ECOG performance status at screening was 0 in 41% of patients, 1 in 58% of patients, and 2 in 1.5% of patients.

Serious adverse reactions occurred in 46% of patients. The most common nonlaboratory serious adverse reactions (> 2%) were CRS, encephalopathy, sepsis, febrile neutropenia, aphasia, pneumonia, fever, hypotension, dizziness, and delirium. Fatal adverse reactions occurred in 4% of patients.

Table 8 presents selected nonlaboratory adverse reactions reported in patients treated with BREYANZI, and Table 9 describes selected new or worsening Grade 3 or 4 laboratory abnormalities.

The most common nonlaboratory adverse reactions (≥ 20%) were fatigue, CRS, musculoskeletal pain, nausea, headache, encephalopathy, infections (pathogen unspecified), decreased appetite, diarrhea, hypotension, tachycardia, dizziness, cough, constipation, abdominal pain, vomiting, and edema.

Table 8: Adverse Reactions in ≥ 10% of Patients with Relapsed or Refractory LBCL Treated with BREYANZI in Study 3 (N=268)
Adverse Reaction | Any Grade (%) | Grade 3 or Higher (%)
Cardiac disorders
Tachycardia* | 25 | 0
Gastrointestinal disorders
Nausea | 33 | 1.5
Diarrhea | 26 | 0.4
Constipation | 23 | 0
Abdominal pain* | 21 | 3.0
Vomiting | 21 | 0.4
General disorders and administration site conditions
Fatigue* | 48 | 3.4
Edemaa | 21 | 1.1
Fever | 16 | 0
Chills | 12 | 0
Immune system disorders
Cytokine release syndrome | 46 | 4.1
Infections and infestations*
Infection with pathogen unspecified* | 29 | 16
Bacterial infection* | 13 | 5
Upper respiratory tract infection* | 13 | 0.7
Viral infection | 10 | 1.5
Metabolism and nutrition disorders
Decreased appetite | 28 | 2.6
Musculoskeletal and connective tissue disorders
Musculoskeletal pain* | 37 | 2.2
Nervous system disorders
Headache* | 30 | 1.1
Encephalopathyb | 29 | 9
Dizzinessc | 24 | 2.6
Tremord | 16 | 0
Peripheral neuropathye | 11 | 0
Aphasiaf | 10 | 2.2
Motor dysfunctiong | 10 | 1.1
Psychiatric disorders
Insomnia* | 14 | 0.4
Anxiety* | 10 | 0
Deliriumh | 10 | 2.2
Renal and urinary disorders
Renal failure* | 11 | 3.0
Respiratory, thoracic, and mediastinal disorders
Cough* | 23 | 0
Dyspnea* | 16 | 2.6
Skin and subcutaneous tissue disorders
Rashi | 13 | 0.4
Vascular disorders
Hypotension* | 26 | 3.4
Hypertension | 14 | 4.5
Hemorrhagej | 10 | 1.5
* Represents multiple related terms.
a Edema includes edema, edema peripheral, fluid overload, fluid retention, generalized edema, hypervolemia, peripheral swelling, pulmonary congestion, pulmonary edema, swelling.
b Encephalopathy includes amnesia, bradyphrenia, cognitive disorder, confusional state, depersonalization/derealization disorder, depressed level of consciousness, disturbance in attention, encephalopathy, flat affect, hypersomnia, incoherent, lethargy, leukoencephalopathy, loss of consciousness, memory impairment, mental impairment, mental status changes, somnolence.
c Dizziness includes dizziness, presyncope, syncope, vertigo.
d Tremor includes essential tremor, resting tremor, tremor.
e Peripheral neuropathy includes hyperesthesia, hypoesthesia, meralgia paresthetica, neuralgia, neuropathy peripheral, paresthesia, peripheral sensory neuropathy, sciatica, sensory loss.
f Aphasia includes aphasia, disorganized speech, dysarthria, dysphemia, dysphonia, slow speech, speech disorder.
g Motor dysfunction includes eyelid ptosis, motor dysfunction, muscle rigidity, muscle spasms, muscle spasticity, muscle tightness, muscle twitching, muscular weakness, myoclonus, myopathy.
h Delirium includes agitation, delirium, delusion, disorientation, hallucination, ‘hallucination, visual’, irritability, restlessness.
i Rash includes erythema, dermatitis acneiform, perineal rash, rash, rash erythematous, rash macular, rash maculo-papular, rash morbilliform, rash papular, rash pruritic, rash pustular.
j Hemorrhage includes catheter site hemorrhage, conjunctival hemorrhage, epistaxis, hematoma, hematuria, hemorrhage, hemorrhage intracranial, pulmonary hemorrhage, retinal hemorrhage, vaginal hemorrhage.

Other clinically important adverse reactions in < 10% of patients included the following:

- Cardiac disorders: Arrhythmia (6%), cardiomyopathy (1.5%)
- Gastrointestinal disorders: Gastrointestinal hemorrhage (4.1%)
- Infections and infestations: Pneumonia (8%), fungal infection (8%), sepsis (4.5%), urinary tract infection (4.1%)
- Metabolism and nutrition disorders: Tumor lysis syndrome (0.7%)
- Nervous system disorders: Ataxia or gait disturbance (7%), visual disturbance (5%), paresis (2.6%), cerebrovascular events (1.9%), seizure (1.1%), brain edema (0.4%)
- Procedural complications: Infusion-related reaction (1.9%)
- Respiratory, thoracic, and mediastinal disorders: Pleural effusion (7%), hypoxia (6%)
- Vascular disorder: Thrombosis (7%)

Table 9: Grade 3 or 4 Laboratory Abnormalities Occurring in ≥ 10% of Patients with Relapsed or Refractory LBCL Treated with BREYANZI in Study 3
Laboratory Abnormalitya | Grade 3 or 4 (%)b
Lymphocyte count decreased | 95
Neutrophil count decreased | 88
Platelet count decreased | 41
Hemoglobin decreased | 32
Phosphate decreased | 16
Fibrinogen decreased | 14
a Baseline lab values were assessed prior to lymphodepleting chemotherapy.
b The denominator varied from 239 to 268, based on the number of patients with a baseline value and at least one post-treatment value for the particular lab.

Study 4 (017004; Relapsed or Refractory CLL/SLL)

Study 4 was an open-label, single-arm study which evaluated 89 adult patients with R/R CLL/SLL who had received at least 2 prior lines of therapy including a BTK inhibitor and a BCL-2 inhibitor before receiving a single dose of CAR positive viable T cells [see Clinical Studies (14.2)]. Patients with a history of CNS disorders (such as seizures or cerebrovascular ischemia) or autoimmune disease requiring systemic immunosuppression, Richter’s transformation, ECOG performance status >1 were ineligible. The trial required LVEF ≥ 40%, adequate oxygen saturation on room air with ≤ Grade 1 dyspnea, ALT ≤ 5 x ULN, total bilirubin < 2.0 mg/dL, creatinine clearance > 30 mL/min, and adequate bone marrow function to receive lymphodepleting chemotherapy.

The median age of the study population was 66 years (range: 49 to 82 years); 69% were male, 84% were White, 3% were Black, 1% were Asian. Two percent were Hispanic, and 89% were non-Hispanic. The ECOG performance status at screening was 0 in 40% of patients, and 1 in 60% of patients.

Serious adverse reactions occurred in 60% of patients. The most common nonlaboratory serious adverse reactions (> 2%) were CRS, encephalopathy, febrile neutropenia, pneumonia, hemorrhage, fever, renal failure, aphasia, abdominal pain, delirium, tumor lysis syndrome, upper respiratory tract infection, and hemophagocytic lymphohistiocytosis [IEC-HS]. Fatal adverse reactions occurred in 1.1% of patients.

Table 10 presents selected nonlaboratory adverse reactions reported in patients treated with BREYANZI, and Table 11 describes selected new or worsening Grade 3 or 4 laboratory abnormalities.

The most common nonlaboratory adverse reactions (≥ 20%) were CRS, encephalopathy, fatigue, musculoskeletal pain, nausea, edema, diarrhea, dyspnea, headache, fever, decreased appetite, constipation, tremor, dizziness, Infection with pathogen unspecified, rash, tachycardia, cough, and delirium.

Table 10: Adverse Reactions in ≥ 10% of Patients with Relapsed or Refractory CLL/SLL Treated with BREYANZI in Study 4 (N=89)
Adverse Reaction | Any Grade (%) | Grade 3 or Higher (%)
Blood and lymphatic system disorders
Febrile neutropenia | 12 | 12
Cardiac disorders
Tachycardia* | 21 | 0
Gastrointestinal disorders
Nausea | 35 | 0
Diarrhea* | 30 | 1.1
Constipation | 24 | 0
Abdominal pain* | 18 | 0
Vomiting | 15 | 0
General disorders and administration site conditions
Fatigue* | 40 | 4.5
Edemaa | 30 | 4.5
Fever* | 27 | 1.1
Chills | 17 | 1.1
Immune system disorders
Cytokine release syndrome | 83 | 9
Infections and infestations
Infection with pathogen unspecified* | 23 | 10
Upper respiratory tract infection* | 19 | 1.1
Viral infection* | 10 | 1.1
Metabolism and nutrition disorders
Decreased appetite | 27 | 4.5
Tumor lysis syndrome | 11 | 11
Musculoskeletal and connective tissue disorders
Musculoskeletal pain* | 42 | 1.1
Nervous system disorders
Encephalopathyb | 44 | 18
Headache* | 28 | 1.1
Tremor | 24 | 2.2
Dizzinessc | 21 | 1.1
Motor dysfunctiond | 14 | 2.2
Peripheral neuropathye | 12 | 0
Taste disorder* | 10 | 0
Psychiatric disorders
Deliriumf | 20 | 3.4
Insomnia | 16 | 1.1
Anxiety | 12 | 1.1
Renal and urinary disorders
Renal failure* | 15 | 3.4
Respiratory, thoracic, and mediastinal disorders
Dyspnea* | 27 | 8
Cough* | 20 | 0
Skin and subcutaneous tissue disorders
Rashg | 23 | 2.2
Vascular disorders
Hypotension* | 17 | 0
Hemorrhageh | 16 | 1.1
Hypertension | 10 | 4.5
* Represents multiple related terms.
a Edema includes ascites, face edema, hypervolemia, edema peripheral, pleural effusion, pulmonary edema, scrotal edema.
b Encephalopathy includes cognitive disorder, confusional state, disturbance in attention, encephalopathy, lethargy, memory impairment, mental status changes, somnolence.
c Dizziness includes dizziness, presyncope, syncope, vertigo.
d Motor dysfunction includes asterixis, muscle spasms, muscular weakness, myoclonus.
ePeripheral neuropathy includes hyperesthesia, hypoesthesia, neuralgia, neuropathy peripheral, paresthesia, peripheral sensory neuropathy.
f Delirium includes agitation, delirium, hallucination, hallucination visual, intensive care unit delirium, irritability, restlessness.
g Rash includes dermatitis contact, erythema, petechiae, rash, rash macular, rash maculo-papular, scrotal erythema, seborrheic keratosis, urticaria.
hHemorrhage includes epistaxis, hemorrhage intracranial, hematoma, hematuria, hemorrhoidal hemorrhage, intraventricular hemorrhage, lower gastrointestinal hemorrhage, traumatic hemothorax.

Other clinically important adverse reactions in < 10% of patients included the following:

- Cardiac disorders: Chest discomfort (4.5%), Arrhythmia (2.2%).
- Eye disorders: Vision blurred (4.5%).
- Gastrointestinal disorders: Dyspepsia (9%), abdominal distension (7%).
- Immune system disorders: Hemophagocytic lymphohistiocytosis [IEC-HS] (3.4%).
- Infections and infestations: Fungal infection (9%), pneumonia (7%), urinary tract infection (7%), bacterial infectious disorders (4.5%), sepsis (2.2%).
- Injury, poisoning and procedural complications: Infusion related reaction (1.1%).
- Nervous system disorders: Aphasia (8%), Ataxia (3.4%), Paresis (3.4%), Seizure (1.1%).
- Psychiatric disorders: Affective disorder (7%).
- Respiratory, thoracic, and mediastinal disorders: Oral pain (8%), hypoxia (8%).
- Skin and subcutaneous tissue disorders: Ecchymosis (8%), xerosis (7%), pruritus (6%).
- Vascular disorder: Thrombosis (6%).

Table 11: Grade 3 or 4 Laboratory Abnormalities Occurring in ≥ 10% of Patients with Relapsed or Refractory CLL/SLL Treated with BREYANZI in Study 4
Laboratory Abnormalitya | Grade 3 or 4 (%)b
Neutrophil count decreased | 94
Lymphocyte count decreased | 87
White blood cell decreased | 85
Platelet count decreased | 53
Hemoglobin decreased | 49
Hypophosphatemia | 24
Hyponatremia | 18
Hypocalcemia | 11
a Baseline lab values were assessed prior to lymphodepleting chemotherapy.
b The denominator ranged from 85 to 89 for other measurements, based on the number of patients with a baseline value and at least one post-treatment value for the particular lab.

Grade 4 laboratory abnormalities in ≥ 10% of patients were neutrophil count decreased (81%), lymphocyte count decreased (73%), white blood cell decreased (72%), and platelet count decreased (30%).

Study 5 (JCAR017-FOL-001; Relapsed or Refractory FL Cohort)

Study 5 was an open-label, single-arm study which evaluated 107 adult patients with relapsed or refractory FL after two or more prior lines of therapy received a single dose of BREYANZI [see Clinical Studies (14.3)]. Patients with a history of CNS disorders and active autoimmune disease requiring immunosuppressive therapy were ineligible. The median age was 62 years (range: 23 to 80 years), 38 % were female, and ECOG performance status was 0 in 61% and 1 in 39% of patients; 56% were White, 3% were Black, 9% were Asian; 5% were Hispanic and 69% were non-Hispanic.

Serious adverse reactions occurred in 26% of patients. The most common nonlaboratory serious adverse reactions (> 2%) were CRS, aphasia, febrile neutropenia, fever, and tremor.

Table 12 presents selected nonlaboratory adverse reactions reported in patients treated with BREYANZI, and Table 13 describes selected new or worsening Grade 3 or 4 laboratory abnormalities.

The most common nonlaboratory adverse reactions (≥ 20%) were CRS, headache, musculoskeletal pain, fatigue, constipation, and fever.

Table 12: Adverse Reactions** in ≥ 10% of Patients with Relapsed or Refractory FL Treated with BREYANZI in Study 5 (N=107)
Adverse Reaction | Any Grade (%) | Grade 3 or Higher (%)
Gastrointestinal disorders
Constipation | 21 | 0
Diarrhea | 15 | 0
General disorders and administration site conditions
Fatigue* | 23 | 0
Fever* | 20 | 0
Immune system disorders
Cytokine release syndrome | 59 | 0.9
Infections and infestations
Infection with pathogen unspecified* | 16 | 4.7
Musculoskeletal and connective tissue disorders
Musculoskeletal pain* | 28 | 0
Nervous system disorders
Headache | 28 | 0
Tremor | 15 | 0
* Represents multiple related terms.
** Includes adverse reactions up to 90 days following treatment with BREYANZI.

Other clinically important adverse reactions in < 10% of patients included the following:

- Blood and lymphatic system disorders: Febrile neutropenia (6%).
- Cardiac disorders: Tachycardia (2.8%).
- Eye disorders: Vision blurred (1.9%).
- Gastrointestinal disorders: Nausea (9%), abdominal pain (4.7%), vomiting (3.7%).
- General disorders and administration site conditions: Edema (4.7%), chills (3.7%).
- Infections and infestations: Upper respiratory tract infection (8%), bacterial infectious disorders (6%), urinary tract infection (4.7%), viral infectious disorders (1.9%), pneumonia (1.9%), sepsis (0.9%).
- Nervous system disorders: Encephalopathy (7%), aphasia (8%), dizziness (4.7%), motor dysfunction (3.7%), ataxia (3.7%), neuropathy peripheral (4.7%).
- Psychiatric disorders: Insomnia (4.7%), delirium (4.7%), anxiety (1.9%).
- Renal and urinary disorders: Acute kidney injury (0.9%).
- Respiratory, thoracic and mediastinal disorders: Cough (7%), dyspnea (1.9%), hypoxia (1.9%).
- Vascular disorders: Hypotension (8%), hypertension (6%), thrombosis (4.7%).
- Skin and subcutaneous tissue disorders: Rash (7%).

Table 13: Grade 3 or 4 Laboratory Abnormalities* Occurring in ≥ 10% of Patients with Relapsed or Refractory FL Treated with BREYANZI in Study 5 (N=107)
Laboratory Abnormalitya | Grade 3 or 4 (%)b
Lymphocyte count decreased | 94
Neutrophil count decreased | 79
White blood cell decreased | 74
Platelet count decreased | 17
* Includes laboratory abnormalities up to 90 days following treatment with BREYANZI.
a Baseline lab values were assessed prior to lymphodepleting chemotherapy.
b Based on the number of patients with a baseline value and at least one post treatment value for the particular lab.

Grade 4 laboratory abnormalities in ≥ 10% of patients were lymphocyte count decreased (78%), neutrophil count decreased (61%), white blood cell decreased (41%), and platelet count decreased (11%).

Study 3 (017001; Relapsed or Refractory MCL Cohort)

Study 3 was an open-label, single-arm study which evaluated 88 adult patients with relapsed or refractory MCL received a single dose of CAR-positive viable T cells [see Clinical Studies (14.4)]. Patients with a history of CNS disorders (such as seizures or cerebrovascular ischemia) or autoimmune disease requiring systemic immunosuppression were ineligible. The trial required left ventricular ejection fraction ≥ 40%, adequate oxygen saturation on room air with ≤ Grade 1 dyspnea, ALT ≤ 5 x ULN, total bilirubin < 2.0 mg/dL, creatinine clearance > 30 mL/min, and adequate bone marrow function to receive lymphodepleting chemotherapy. The median age of the study population was 69 years (range: 36 to 86 years); 76% were male, 88% were White, 6% were Asian and 2.3% were Black. Four percent were Hispanic, and 92% were non-Hispanic. The ECOG performance status at screening was 0 in 54% of patients, and 1 in 46% of patients.

Serious adverse reactions occurred in 53% of patients. The most common nonlaboratory serious adverse reactions (> 2%) were CRS, confusional state, fever, encephalopathy, mental status changes, pleural effusion, upper respiratory tract infection, and decreased appetite. Fatal adverse reactions occurred in 4.5% of patients.

Table 14 presents selected nonlaboratory adverse reactions reported in patients treated with BREYANZI, and Table 15 describes selected new or worsening Grade 3 or 4 laboratory abnormalities.

The most common nonlaboratory adverse reactions (≥ 20%) were CRS, fatigue, musculoskeletal pain, encephalopathy, edema, headache, and decreased appetite.

Table 14: Adverse Reactions** in ≥ 10% of Patients with Relapsed or Refractory MCL Treated with BREYANZI in Study 3 (N=88)
Adverse Reaction | Any Grade (%) | Grade 3 or Higher (%)
Cardiac disorders
Tachycardia* | 17 | 3.4
Gastrointestinal disorders
Nausea | 18 | 2.3
Diarrhea | 17 | 0
Abdominal pain* | 15 | 3.4
Constipation | 14 | 0
General disorders and administration site conditions
Fatigue* | 39 | 2.3
Edemaa | 25 | 1.1
Fever* | 17 | 0
Chills | 11 | 0
Immune system disorders
Cytokine release syndrome | 61 | 1.1
Infections and infestations
Infection with pathogen unspecified* | 16 | 6
Upper respiratory tract infection* | 13 | 2.3
Metabolism and nutrition disorders
Decreased appetite | 21 | 4.5
Musculoskeletal and connective tissue disorders
Musculoskeletal pain* | 38 | 2.3
Nervous system disorders
Encephalopathyb | 30 | 9
Headache | 23 | 0
Dizzinessc | 11 | 2.3
Motor dysfunctiond | 11 | 0
Tremor | 11 | 0
Psychiatric disorders
Insomnia* | 14 | 0
Anxiety | 13 | 1.1
Renal and urinary disorders
Renal failure* | 15 | 0
Respiratory, thoracic, and mediastinal disorders
Dyspnea* | 11 | 0
Cough | 10 | 0
Skin and subcutaneous tissue disorders
Rashe | 11 | 1.1
Vascular disorders
Hypotension* | 15 | 0
Hemorrhagef | 10 | 0
Hypertension | 10 | 3.4
* Represents multiple related terms.
** Includes adverse reactions up to 90 days following treatment with BREYANZI.
a Edema includes hypervolemia, localized edema, edema, edema peripheral, peripheral swelling, pleural effusion, pulmonary edema.
b Encephalopathy includes confusional state, depressed level of consciousness, encephalopathy, lethargy, memory impairment, mental status changes, somnolence.
c Dizziness includes dizziness, dizziness postural, syncope, vertigo.
d Motor dysfunction includes fine motor skill dysfunction, muscle spasms, muscle tightness, muscular weakness.
e Rash includes dermatitis contact, rash, rash erythematous, rash macular, rash maculo-papular, rash pruritic.
f Hemorrhage includes catheter site hemorrhage, epistaxis, hematoma, hematuria, hemorrhage, hemorrhoidal hemorrhage, rectal hemorrhage.

Other clinically important adverse reactions in < 10% of patients included the following:

- Blood and lymphatic system disorders: Febrile neutropenia (6%).
- Cardiac disorders: Arrhythmia (2.3%).
- Eye disorders: Vision blurred (3.4%).
- Gastrointestinal disorders: Vomiting (6%).
- Infections and infestations: Bacterial infection (9%), viral infection (9%), fungal infection (8%), urinary tract infection (6%), sepsis (3.4%), pneumonia (2.3%).
- Injury, poisoning and procedural complications: Infusion related reaction (4.5%).
- Metabolism and nutrition disorders: Tumor lysis syndrome (2.3%).
- Nervous system disorders: Neuropathy peripheral (9%), aphasia (8%), ataxia (4.5%), cerebral infarction (1.1%), seizure (1.1%).
- Psychiatric disorders: Delirium (7%).
- Respiratory, thoracic, and mediastinal disorders: Hypoxia (3.4%).
- Vascular disorder: Thrombosis (4.5%).

Table 15: Grade 3 or 4 Laboratory Abnormalities* Occurring in ≥ 10% of Patients with Relapsed or Refractory MCL Treated with BREYANZI in Study 3
Laboratory Abnormalitya | Grade 3 or 4 (%)b
Lymphocyte count decreased | 89
Neutrophil count decreased | 85
White blood cell decreased | 83
Platelet count decreased | 39
Hemoglobin decreased | 33
Uric acid increased | 10
Sodium decreased | 10
* Includes lab abnormalities up to 90 days following treatment with BREYANZI.
a Baseline lab values were assessed prior to lymphodepleting chemotherapy.
b The denominator ranged from 87 to 88 for laboratory measurements, based on the number of patients with a baseline value and at least one post-treatment value for the particular lab.

Grade 4 laboratory abnormalities in ≥ 10% of patients were lymphocyte count decreased (84%), neutrophil count decreased (52%), white blood cell decreased (52%), and platelet count decreased (22%).

Study 5 (JCAR017-FOL-001; Relapsed or Refractory MZL Cohort)

Study 5 was a an open-label, single-arm study which evaluated 67 adult patients with relapsed or refractory MZL after two or more prior lines of therapy or relapsed after hematopoietic stem cell transplant (HSCT) received a single dose of CAR-positive viable T cells [see Clinical Studies (14.5)]. Patients who had previously received CD19-directed therapy had to have biopsy proven CD19 positive lymphoma [see Clinical Studies (14)]. Patients with a history of CNS disorders (such as seizures or cerebrovascular ischemia) and active autoimmune disease requiring immunosuppressive therapy were ineligible. The median age was 62 years (range: 37 to 81 years), 58% were male, ECOG performance status was 0 in 55% and 1 in 45% of patients; 57% were White, 6% were Asian, 2% were Black; race was not reported in 36% of patients; and 2% were Hispanic.

Serious adverse reactions occurred in 39% of patients. The most common nonlaboratory serious adverse reactions (> 2%) were CRS, encephalopathy, aphasia, sepsis, tremor, delirium, dizziness, infusion related hypersensitivity reaction, and transient ischemic attack. Fatal adverse reactions occurred in 3% of patients.

Table 16 presents nonlaboratory adverse reactions reported in ≥ 10% of patients treated with BREYANZI, and Table 17 describes selected new or worsening Grade 3 or 4 laboratory abnormalities.

The most common nonlaboratory adverse reactions (≥ 20%) were CRS, diarrhea, fatigue, musculoskeletal pain, and headache.

Table 16: Adverse Reactions** in ≥ 10% of Patients with Relapsed or Refractory MZL Treated with BREYANZI in Study 5 (N=67)
Adverse Reaction | Any Grade (%) | Grade 3 or Higher (%)
Gastrointestinal disorders
Diarrhea | 28 | 1.5
Nausea | 18 | 1.5
Abdominal pain* | 10 | 0
General disorders and administration site conditions
Fatigue* | 27 | 3
Edemaa | 18 | 3
Fever* | 10 | 0
Immune system disorders
Cytokine release syndrome | 76 | 4.5
Infections and infestations
Infection with pathogen unspecified* | 16 | 6
Metabolism and nutrition disorders
Decreased appetite | 10 | 3
Musculoskeletal and connective tissue disorders
Musculoskeletal pain* | 22 | 0
Nervous system disorders
Headache | 21 | 1.5
Tremor | 21 | 0
Encephalopathyb | 21 | 1.5
Dizziness | 16 | 0
Aphasia | 10 | 0
Psychiatric disorders
Deliriumc | 10 | 3
Renal and urinary disorders
Renal failure* | 10 | 1.5
Vascular disorders
Hypotension | 10 | 0
* Represents multiple related terms.
** Includes adverse reactions up to 90 days following treatment with BREYANZI.
a Edema includes ascites, fluid retention, hypervolaemia, oedema peripheral, peripheral swelling, pleural effusion, pulmonary oedema.
b Encephalopathy includes brain fog, cognitive disorder, confusional state, disturbance in attention, dyscalculia, dysgraphia, memory impairment, somnolence.
c Delirium includes delirium, disorientation, hallucination, irritability, restlessness.

Other clinically important adverse reactions in < 10% of patients included the following:

- Blood and lymphatic system disorders: Febrile neutropenia (3%).
- Cardiac disorders: Tachycardia (7.5%).
- Gastrointestinal disorders: Vomiting (9%), constipation (3%), dyspepsia (3%).
- General disorders and administration site conditions: Chills (7.5%), infusion related hypersensitivity reactions (3%).
- Immune system disorders: Hemophagocytic lymphohistiocytosis (4.5%).
- Infections and infestations: Bacterial infections (6%), viral infections (6%), fungal infections (3%).
- Metabolism and nutrition disorders: Tumor lysis syndrome (1.5%).
- Nervous system disorders: Motor dysfunction (4.5%), ataxia (3%), neuropathy peripheral (3%), transient ischaemic attack (3.0%).
- Psychiatric disorders: Insomnia (9%), affective disorder (7.5%).
- Respiratory, thoracic and mediastinal disorders: Dyspnea (6%), cough (4.5%), hypoxia (4.5%).
- Skin and subcutaneous tissue disorders: Rash (4.5%).
- Vascular disorders: Hemorrhage (9%), hypertension (6%), thrombosis (6%).

Table 17: Grade 3 or 4 Laboratory Abnormalities* Occurring in ≥ 10% of Patients with Relapsed or Refractory MZL Treated with BREYANZI in Study 5 (N=67)
Laboratory Abnormalitya | Grade 3 or 4 (%)b
Lymphocyte count decreased | 99
Neutrophil count decreased | 84
White blood cell decreased | 84
Platelet count decreased | 28
Hemoglobin decreased | 25
Fibrinogen decreased | 10
* Includes laboratory abnormalities up to 90 days following treatment with BREYANZI.
a Baseline lab values were assessed prior to lymphodepleting chemotherapy.
b Based on the number of patients with a baseline value and at least one post treatment value for the particular lab.

Grade 4 laboratory abnormalities in ≥ 10% of patients were lymphocyte count decreased (85%), neutrophil count decreased (64%), white blood cell decreased (49%), and platelet count decreased (19%).

6.2 Postmarketing Experience

Because adverse events to marketed products are reported voluntarily from a population of uncertain size, it is not always possible to reliably estimate their frequency or establish a causal relationship to product exposure.

The following adverse events have been identified during postmarketing use of BREYANZI.

Nervous System Disorder: Immune effector cell-associated neurotoxicity syndrome (ICANS).

Neoplasms: T cell malignancies

Eye disorders: Blindness

7 DRUG INTERACTIONS

7.1 Drug-Laboratory Test Interactions

HIV and the lentivirus used to make BREYANZI have limited, short spans of identical genetic material (RNA). Therefore, some commercial HIV nucleic acid tests may yield false-positive results in patients who have received BREYANZI.

8 USE IN SPECIFIC POPULATIONS

8.1 Pregnancy

Risk Summary

There are no available data with BREYANZI use in pregnant women. No animal reproductive and developmental toxicity studies have been conducted with BREYANZI to assess whether it can cause fetal harm when administered to a pregnant woman.

It is not known if BREYANZI has the potential to be transferred to the fetus. Based on the mechanism of action, if the transduced cells cross the placenta, they may cause fetal toxicity, including B-cell lymphocytopenia and hypogammaglobulinemia. Therefore, BREYANZI is not recommended for women who are pregnant, and pregnancy after BREYANZI infusion should be discussed with the treating physician.

In the U.S. general population, the estimated background risk of major birth defects and miscarriage in clinically recognized pregnancies is 2% to 4% and 15% to 20%, respectively.

8.2 Lactation

Risk Summary

There is no information regarding the presence of BREYANZI in human milk, the effect on the breastfed infant, and the effects on milk production. The developmental and health benefits of breastfeeding should be considered along with the mother’s clinical need for BREYANZI and any potential adverse effects on the breastfed infant from BREYANZI or from the underlying maternal condition.

8.3 Females and Males of Reproductive Potential

Pregnancy Testing

Pregnancy status of females with reproductive potential should be verified. Sexually active females of reproductive potential should have a pregnancy test prior to starting treatment with BREYANZI.

Contraception

See the prescribing information for fludarabine and cyclophosphamide for information on the need for effective contraception in patients who receive lymphodepleting chemotherapy.

There are insufficient exposure data to provide a recommendation concerning duration of contraception following treatment with BREYANZI.

Infertility

There are no data on the effects of BREYANZI on fertility.

8.4 Pediatric Use

The safety and efficacy of BREYANZI have not been established in pediatric patients.

8.5 Geriatric Use

In clinical trials of BREYANZI, 111 (41%) of 268 patients with two or more prior lines of therapy for LBCL, and 89 (59%) of 150 patients with one prior line of therapy for LBCL, were 65 years of age or older; 27 (10%) and 28 (19%) were 75 years of age or older, respectively. In patients with CLL/SLL, 51 (57%) of 89 were 65 years of age or older, and 9 (10%) were 75 years of age or older. In patients with FL, 42 (39%) of 107 were 65 years of age or older, and 10 (9%) were 75 years of age or older. In patients with MCL, 64 (73%) of 88 patients were 65 years of age or older, and 18 (21%) were 75 years of age or older. In patients with MZL, 30 (45%) of 67 patients were 65 years of age or older, and 10 (15%) were 75 years of age or older. No clinically important differences in safety or effectiveness of BREYANZI were observed between patients aged ≥ 65 and younger patients.

11 DESCRIPTION

BREYANZI (lisocabtagene maraleucel) is a CD19-directed genetically modified autologous T cell immunotherapy administered as a defined composition of CAR-positive viable T cells (consisting of CD8 and CD4 components). The CAR is comprised of the FMC63 monoclonal antibody-derived single-chain variable fragment (scFv), IgG4 hinge region, CD28 transmembrane domain, 4-1BB (CD137) costimulatory domain, and CD3 zeta activation domain. In addition, BREYANZI includes a nonfunctional truncated epidermal growth factor receptor (EGFRt) that is co-expressed on the cell surface with the CD19-specific CAR.

BREYANZI is a T cell product. BREYANZI is prepared from the patient’s T cells, which are obtained via a standard leukapheresis procedure. The purified CD8-positive and CD4-positive T cells are separately activated and transduced with the replication-incompetent lentiviral vector containing the anti-CD19 CAR transgene. The transduced T cells are expanded in cell culture, washed, formulated into a suspension, and cryopreserved as separate CD8 and CD4 component vials that together constitute a single dose of BREYANZI. The product must pass a sterility test before release for shipping as a frozen suspension in patient-specific vials. The product is thawed prior to administration [see Dosage and Administration (2.2) and How Supplied/Storage and Handling (16)].

The BREYANZI formulation contains 75% (v/v) Cryostor® CS10 [containing 7.5% dimethylsulfoxide (v/v)], 24% (v/v) Multiple Electrolytes for Injection, Type 1, 1% (v/v) of 25% albumin (human).

12 CLINICAL PHARMACOLOGY

12.1 Mechanism of Action

BREYANZI is a CD19-directed genetically modified autologous cell immunotherapy administered as a defined composition to reduce variability in CD8-positive and CD4-positive T cell dose. The CAR is comprised of an FMC63 monoclonal antibody-derived single chain variable fragment (scFv), IgG4 hinge region, CD28 transmembrane domain, 4-1BB (CD137) costimulatory domain, and CD3 zeta activation domain. CD3 zeta signaling is critical for initiating activation and antitumor activity, while 4-1BB (CD137) signaling enhances the expansion and persistence of BREYANZI.

CAR binding to CD19 expressed on the cell surface of tumor and normal B cells induces activation and proliferation of CAR T cells, release of pro-inflammatory cytokines, and cytotoxic killing of target cells.

12.2 Pharmacodynamics

Following BREYANZI infusion, pharmacodynamic responses were evaluated over a 4-week period by measuring transient elevation of soluble biomarkers such as cytokines, chemokines, and other molecules. Peak elevation of soluble biomarkers was observed within the first 14 days after BREYANZI infusion and returned to baseline levels within 28 days.

B-cell aplasia, defined as CD19+ B cells comprising less than 3% of peripheral blood lymphocytes, is an on-target effect of BREYANZI. B-cell aplasia was observed in the majority of patients for up to 1 year following BREYANZI infusion.

12.3 Pharmacokinetics

Following infusion, BREYANZI exhibited an initial expansion followed by a bi-exponential decline.

Relapsed or Refractory LBCL

The median time of maximal expansion in peripheral blood occurred 10-12 days after infusion. BREYANZI was present in peripheral blood for an estimated median of 12.1 months (range: 0.1+ to 24.2+ months).

Among patients who received two or more prior lines of therapy for LBCL (Study 3 – LBCL Cohort), responders (N=135) had a 2.3-fold higher median Cmax than nonresponders (N=37) (35,335 vs. 15,527 copies/µg). Responders had a 1.8-fold higher median AUC0-28d than nonresponders (273,552 vs. 155,240 day*copies/µg).

Patients < 65 years old (N=142) had a 3.1-fold and 2.3-fold higher median Cmax and AUC0-28d, respectively, compared to patients ≥ 65 years old (N=96). Sex, race, ethnicity, and body weight did not show clear relationships to Cmax and AUC0-28d.

Relapsed or Refractory CLL/SLL

The median time of maximal expansion in peripheral blood occurred 14 days after infusion. BREYANZI was present in peripheral blood for an estimated median of 12.0 months (range: 0.1+ to 30.1+ months).

Among patients who received prior therapy for CLL/SLL (Study 4), responders (N=27) had a 2.0-fold higher median Cmax than nonresponders (N=25) (99,559 vs. 48,948 copies/µg). Responders had a 1.9-fold higher median AUC0-28d than nonresponders (793,893 vs. 408,307 day*copies/µg).

Relapsed or Refractory FL

The median time of maximal expansion in peripheral blood occurred 10 days after infusion. Median Cmax and AUC0-28d are 30,530 copies/µg and 253,400 day*copies/µg, respectively. BREYANZI was present in peripheral blood for an estimated median of 12.0 months (range: 0.3+ to 24.0+ months).

Relapsed or Refractory MCL

The median time of maximal expansion in peripheral blood occurred 10 days after infusion. Median Cmax and AUC0-28d were 30,968 copies/µg and 375,006 day*copies/µg, respectively. BREYANZI was present in peripheral blood for an estimated median of 17.9 months (range: 0.1+ to 24.2+ months).

Relapsed or Refractory MZL

The median time of maximal expansion in peripheral blood occurred 10 days after infusion. Median Cmax and AUC0-28d were 81,390 copies/µg and 657,799 day*copies/µg, respectively. BREYANZI was present in peripheral blood for an estimated median of 18.0 months (range: 0.6 to 42.1 months).

Patients receiving medications for CRS and/or neurologic toxicities

In general, patients with higher CAR-T cell expansion tended to have higher rates of CRS and neurologic toxicities. Some patients required tocilizumab and/or corticosteroids for the management of CRS or neurologic toxicities [see Dosage and Administration (2.3)]. BREYANZI continued to expand and persist in patients who received tocilizumab and/or corticosteroids treatment. In Study 3 - LBCL Cohort, patients treated with tocilizumab (N=49) had a 3.6-fold and 3.7-fold higher median Cmax and AUC0-28d of BREYANZI, respectively, compared to patients who did not receive tocilizumab (N=189). Similarly, patients who received corticosteroids (N=50) had a 3.8-fold and 3.7-fold higher median Cmax and AUC0‑28d of BREYANZI, respectively, compared to patients who did not receive corticosteroids (N=188).

12.6 Immunogenicity

The observed incidence of anti-product antibodies is highly dependent on the sensitivity and specificity of the assay. Differences in assay methods preclude meaningful comparisons of the incidence of anti-product antibodies in the studies described below with the incidence of anti-product antibodies in other studies, including those of BREYANZI or of other similar products.

BREYANZI has the potential to induce anti-product antibodies. The immunogenicity of BREYANZI has been evaluated using an electrochemiluminescence (ECL) immunoassay for the detection of binding antibodies against the extracellular CD19-binding domain of BREYANZI. Pre-existing anti-product antibodies were detected in 11% (28/261) in Study 3 - LBCL Cohort, 1% (1/89) in Study 1, 0% (0/51) in Study 2, 2% (2/86) in Study 4, 2% (2/102) in Study 5 - FL Cohort, 13% (11/87) in Study 3 - MCL Cohort, and 0% (0/66) in Study 5 - MZL Cohort of patients. Treatment-induced or treatment-boosted anti-product antibodies were detected in 11% (27/257) in Study 3 - LBCL Cohort, 1% (1/89) in Study 1, 2% (1/49) in Study 2, 7% (6/84) in Study 4, 18% (18/100) in Study 5 - FL Cohort, 18% (15/85) in Study 3 - MCL Cohort, and 20% (13/66) in Study 5 - MZL Cohort of patients. Due to the small number of patients who had anti-product antibodies, the relationship between anti-product antibody status and efficacy, safety, or pharmacokinetics was not conclusive.

13 NONCLINICAL TOXICOLOGY

13.1 Carcinogenesis, Mutagenesis, Impairment of Fertility

No carcinogenicity or genotoxicity studies have been conducted with BREYANZI. No studies have been conducted to evaluate the effects of BREYANZI on fertility. In vitro studies with BREYANZI manufactured from healthy donors and patients showed no evidence for transformation and/or immortalization and no preferential integration near genes associated with oncogenic transformation.

14 CLINICAL STUDIES

14.1 Relapsed or Refractory Large B-Cell Lymphoma

Relapsed or Refractory LBCL After One Line of Therapy

Study 1

A randomized, open-label, multicenter trial evaluated the efficacy of BREYANZI in adult patients with relapsed or refractory LBCL after first-line chemoimmunotherapy (Study 1: JCAR017-BCM-003; NCT03575351). Patients had not yet received treatment for relapsed or refractory lymphoma, were potential candidates for autologous HSCT, and were required to have primary refractory disease or relapse within 12 months from complete response (CR) to initial chemoimmunotherapy. Eligibility criteria required adequate organ function and blood counts for HSCT.

In total, 184 patients were randomized in a 1:1 ratio to receive a single infusion of BREYANZI (planned dose, 100 × 10^6 CAR-positive viable T cells) or to receive standard therapy consisting of 3 cycles of chemoimmunotherapy followed by high-dose therapy and autologous HSCT in patients who attained CR or PR. All patients underwent leukapheresis prior to randomization.

Patients randomized to BREYANZI were to receive lymphodepleting chemotherapy consisting of fludarabine 30 mg/m^2/day and cyclophosphamide 300 mg/m^2/day concurrently for 3 days followed by BREYANZI infusion 2 to 7 days after completion of lymphodepleting chemotherapy. Bridging chemotherapy was permitted between leukapheresis and the start of lymphodepleting chemotherapy. BREYANZI was administered in the inpatient (79%) and outpatient (21%) setting.

In the overall study population, the median age was 59 years (range: 20 to 75 years), 57% were male, 59% were White, 10% were Asian, and 4% were Black. Diagnoses included de novo DLBCL NOS (55%), high-grade B-cell lymphoma (23%), primary mediastinal large B-cell lymphoma (10%), and DLBCL arising from indolent lymphoma (8%). Of these patients, 73% had primary refractory disease to last therapy and 27% had relapsed disease within 12 months of achieving CR to first-line therapy.

Of 92 patients randomized to receive BREYANZI, 89 (97%) received BREYANZI. The median time from leukapheresis to product availability was 26 days (range: 19 to 84 days), and the median time from leukapheresis to product infusion was 36 days (range: 25 to 91 days). Fifty-eight (63%) patients received bridging therapy. One patient received a nonconforming product (manufacturing failure; 1.1%).

Of the 92 patients randomized to receive standard therapy, 91 started treatment and 43 (47%) received high-dose therapy and HSCT. The most common reason for not receiving HSCT was lack of efficacy of the salvage chemotherapy.

The primary efficacy measure was event-free survival (EFS) as determined by an independent review committee (IRC). Other efficacy measures included progression-free survival. Efficacy is summarized in Table 18 and Figure 1. The estimated 1-year EFS was 45% [95% CI: 29, 59] in the BREYANZI arm and 24% [95% CI: 14, 35] in the standard therapy arm.

Of the 92 patients in the BREYANZI arm, the estimated median duration of response (DOR) was not reached (95% CI: 7.9 months, NR) in patients who achieved CR (N=61) and 2.3 months (95% CI: 2.1, NR) in patients who achieved a best response of PR (N=18).

An interim analysis of overall survival was conducted at the time of the primary EFS analysis. The interim analysis of overall survival did not meet the criteria for statistical significance. Forty-six patients randomized to the standard therapy arm (50%) subsequently received BREYANZI on protocol.

Table 18: Efficacy Results in Patients with Relapsed or Refractory LBCL (Study 1)
Outcomea | BREYANZI Arm; (N=92) | Standard Therapy Arm; (N=92)
Event-Free Survivalb
Number of events, n (%) | 35 (38) | 63 (69)
Median, months [95% CI]c | 10.1 [6.1, NR] | 2.3 [2.2, 4.3]
Hazard ratio [95% CI]d | 0.34 [0.22, 0.52]
One-sided p-value | <0.0001f
Complete Response Rate, % [95% CI] | 66 [56, 76] | 39 [29, 50]
Difference in CR rate, % [95% CI] | 27 [12, 41]
One-sided p-valuee | <0.0001f
Progression-Free Survival
Number of events, n (%) | 28 (30) | 43 (47)
Median, months [95% CI]c | 14.8 [6.6, NR] | 5.7 [3.9, 9.4]
Hazard ratio [95% CI]d | 0.41 [0.25, 0.66]
One-sided p-value | 0.0001f
NR=not reached; CI=confidence interval.
a Per the Lugano criteria, as assessed by an IRC.
b EFS is defined as time from randomization to the earliest date of disease progression or relapse, death from any cause, failure to achieve CR or PR by 9 weeks post-randomization, or start of new lymphoma therapy due to efficacy concerns.
c Kaplan-Meier estimate.
d Based on a stratified Cox proportional hazards model. For all stratified analyses, stratification was based on response to first-line therapy (primary refractory vs relapsed) and second-line age-adjusted International Prognostic Index.
e Cochran-Mantel-Haenszel test.
f p-value is compared with 0.012 of the allocated alpha for this pre-specified interim analysis.

Figure 1: Kaplan-Meier Plot of IRC-Assessed Event-Free Survival (Intention-to- Treat Analysis)

Study 2

The efficacy of BREYANZI was evaluated in a single-arm, open-label, multicenter trial (Study 2: 017006; NCT03483103) in transplant-ineligible patients with relapsed or refractory LBCL after one line of chemoimmunotherapy. The study enrolled patients who were not eligible for high-dose therapy and autologous HSCT due to organ function or age, while also having adequate organ function for CAR-T cell therapy. The study required at least one of the following criteria: age ≥ 70 years, adjusted diffusing capacity of the lung for carbon monoxide (DLCO) ≤ 60%; LVEF < 50%; creatinine clearance < 60 mL/min; AST or ALT greater than 2 × ULN, or ECOG performance status of 2. The planned dose of BREYANZI was 100 × 10^6 CAR-positive viable T cells. Bridging therapy for disease control was permitted between leukapheresis and the start of lymphodepleting chemotherapy. Of the 61 patients treated with BREYANZI, 32 (53%) received bridging therapy.

BREYANZI was administered 2 to 7 days following completion of lymphodepleting chemotherapy. The lymphodepleting chemotherapy regimen consisted of fludarabine 30 mg/m^2/day and cyclophosphamide 300 mg/m^2/day concurrently for 3 days. BREYANZI was administered in the inpatient (67%) and outpatient (33%) setting.

Of 74 patients who underwent leukapheresis, 61 (82%) received BREYANZI and comprise the main efficacy population; 1 (1.4%) received CAR-positive T cells that did not meet the product specifications for BREYANZI (manufacturing failure); and 12 (16%) did not receive CAR-positive T cells for other reasons.

Of the 61 patients who received BREYANZI, the median age was 74 years (range: 53 to 84 years), 61% were male, 89% were White, 3% were Asian, and 2% were Black. Diagnoses included de novo DLBCL NOS (51%), high-grade B-cell lymphoma (33%), and DLBCL arising from follicular lymphoma (15%). Of these patients, 53% had primary refractory disease, 23% had relapse within 12 months of completing first-line therapy, and 25% had relapse >12 months after first-line therapy.

Efficacy was based on CR rate and DOR, as determined by an independent review committee (IRC) using 2014 Lugano criteria (Tables 19 and 20). The median time to CR was 1 month (range 0.8 to 6.9 months).

Table 19: Response Rate in Relapsed or Refractory LBCL (Study 2)
Outcomea | BREYANZI-Treated; (N=61) | All Leukapheresed; (N=74)
Overall Response, n (%); [95% CI]b | 49 (80%); [68%, 89%] | 50 (68%); [56%, 78%]
Complete Response; [95% CI] | 33 (54%); [41%, 67%] | 34 (46%); [34%, 58%]
Partial Response; [95% CI] | 16 (26%); [16%, 39%] | 16 (22%); [13%, 33%]
CI=confidence interval; NR=Not reached.
a Per the Lugano criteria, as assessed by an IRC.
b 2-sided 95% exact Clopper-Pearson confidence intervals.

Table 20: Duration of Response in Study 2
Outcomea | BREYANZI-Treated; (N=61)
Number of Responders | 49
DOR
Median [95% CI], months b; Range, months | 11.2 [5.1, NR]; 0.0^+ to 22.8^+
DOR if Best Response is CR; Median [95% CI], months; Range, months; Rate at 6 months [95% CI] c; Rate at 12 months [95% CI] c | NR [11.2, NR]; 2.0^+ to 22.8^+; 83% [64, 93]; 68% [45, 83]
DOR if Best Response is PR
Median [95% CI], months | 2.1 [1.4, 2.3]
Range, months | 0.0^+ to 7.9
Rate at 6 months [95% CI] c | 8.2% [0.5, 30.5]
DOR=duration of response; CI=confidence interval; CR=complete response; PR=partial response; NR=not reached.
a Per the Lugano criteria, as assessed by an IRC.
b Kaplan-Meier method is used to obtain 2-sided 95% confidence intervals.
c Kaplan-Meier estimate.
^+ Indicates a censored value.

Relapsed or Refractory LBCL After Two or More Lines of Therapy

The efficacy of BREYANZI was evaluated in an open-label, multicenter, single-arm trial (Study 3 - LBCL Cohort: 017001; NCT02631044) in adult patients with relapsed or refractory large B-cell non-Hodgkin lymphoma after at least 2 lines of therapy. The study included patients with ECOG performance status ≤ 2, prior autologous and/or allogeneic HSCT, and secondary CNS lymphoma involvement. The study excluded patients with a creatinine clearance of less than 30 mL/min, ALT > 5 times the ULN, or LVEF < 40%. There was no prespecified threshold for blood counts; patients were eligible to enroll if they were assessed by the investigator to have adequate bone marrow function to receive lymphodepleting chemotherapy. Bridging therapy for disease control was permitted between apheresis and the start of lymphodepleting chemotherapy, including intrathecal chemotherapy or radiation therapy for treatment of CNS involvement with lymphoma.

BREYANZI was administered 2 to 7 days following completion of lymphodepleting chemotherapy. The lymphodepleting chemotherapy regimen consisted of fludarabine 30 mg/m^2/day and cyclophosphamide 300 mg/m^2/day concurrently for 3 days. BREYANZI was administered in the inpatient and outpatient setting.

Of 299 patients who underwent leukapheresis for whom BREYANZI was manufactured in the dose range of 50 to 110 × 10^6 CAR-positive viable T cells:

- 44 (15%) did not receive CAR-positive T cells either due to manufacturing failures (n=2), death (n=29), disease complications (n=6), or other reasons (n=7).
- 204 (68%) received BREYANZI in the intended dose range, of whom 192 were evaluable for efficacy (main efficacy population); 12 were not evaluable due to absence of PET positive disease at study baseline or after bridging therapy.
- 51 (17%) either received BREYANZI outside of the intended dose range (n=26) or received CAR-positive T cells that did not meet the product specifications for BREYANZI (manufacturing failures; n=25).

Of the 192 patients in the main efficacy population, the median age was 63 years (range: 18 to 86 years), 69% were male, 84% were White, 6% were Black, and 4.7% were Asian. The median number of prior therapies was 3 (range: 1 to 8). Diagnoses were de novo DLBCL (53%), DLBCL transformed from indolent lymphoma (25%), high-grade B-cell lymphoma (14%), primary mediastinal large B-cell lymphoma (7%), follicular lymphoma, grade 3B (1.0%). Of these patients, 64% had disease refractory to last therapy, 53% had primary refractory disease, 37% had prior HSCT and 2.6% had CNS involvement.

Efficacy was based on CR rate and DOR, as determined by an IRC using 2014 Lugano criteria (Tables 21 and 22). The median time to first response (CR or partial response [PR]) was 1.0 month (range: 0.7 to 8.9 months). The median time to first CR was 1.0 month (range 0.8 to 12.5 months). Of the 104 patients who achieved CR, 23 initially had stable disease (6 patients) or PR (17 patients), with a median time to improvement of 2.2 months (range: 0.7 to 11.6 months).

Table 21: Response Rate in Main Efficacy Population (Study 3 - LBCL Cohort)
 | BREYANZI-Treated N=192
Overall Response Ratea, n [95% CI] | 141 (73%) [67%, 80%]
Complete Response, n [95% CI] | 104 (54%) [47%, 61%]
Partial Response, n [95% CI] | 37 (19%) [14%, 26%]
CI=confidence interval.
a Per the Lugano criteria, as assessed by an IRC.

Table 22: Duration of Response in Study 3 - LBCL Cohort
 | BREYANZI-Treateda N=192
Number of Responders | 141
DOR (Months)
Median [95% CI]b; Range | 16.7 [5.3, NR]; 0.0^+ to 23.5^+
DOR if Best Response is CR (Months)
Median [95% CI]; Range | NR [16.7, NR]; 0.7^+ to 23.5^+
DOR if Best Response is PR (Months)
Median [95% CI]; Range | 1.4 [1.1, 2.2]; 0.0^+ to 22.8^+
DOR=duration of response; CI=confidence interval; CR=complete response; PR=partial response; NR=not reached.
a Evaluable for efficacy.
b KM method was used to obtain 2-sided 95% confidence intervals.
^+ Indicates a censored value.

Response durations were longer in patients who achieved a CR, as compared to patients with a best response of PR (Table 22). Of the 104 patients who achieved CR, 68 (65%) had remission lasting at least 6 months and 64 (62%) had remission lasting at least 9 months.

Of the 287 patients who underwent leukapheresis and had radiographically evaluable disease, 27 additional patients achieved a response, apart from the responses noted in Table 22. The IRC-assessed overall response rate in the leukapheresed population (n=287) was 59% (95% CI: 53, 64), with a CR rate of 43% (95% CI: 37, 49) and PR rate of 15% (95% CI: 11, 20). These efficacy results include responses that may have been contributed solely by bridging therapy, responses after receipt of product outside of the intended dose range, and responses to product that did not meet release specifications.

14.2 Relapsed or Refractory Chronic Lymphocytic Lymphoma or Small Lymphocytic Lymphoma

The efficacy of BREYANZI was evaluated in a phase 1/2, open-label, multicenter, single-arm trial (Study 4: 017004; NCT03331198) in adult patients with R/R CLL or SLL who had received at least 2 prior lines of therapy including a BTK inhibitor and a BCL-2 inhibitor. Patients with del(17p), complex karyotype, and unmutated immunoglobulin heavy chain variable region (IGHV) were included in the study. The study enrolled patients with ECOG performance status of ≤ 1. The study excluded patients with a creatinine clearance of less than 30 mL/min, ALT > 5 times the ULN (except for subjects with leukemic infiltration of the liver), or LVEF < 40%. There was no prespecified threshold for blood counts; patients were eligible to enroll if they were assessed by the investigator to have adequate bone marrow function to receive lymphodepleting chemotherapy. The planned dose of BREYANZI was 100 × 10^6 CAR-positive viable T cells. Bridging therapy for disease control was permitted between apheresis and the start of lymphodepleting chemotherapy.

Of the 89 patients, BREYANZI was administered 2 to 11 days following completion of lymphodepleting chemotherapy. The lymphodepleting chemotherapy regimen consisted of fludarabine 30 mg/m^2/day and cyclophosphamide 300 mg/m^2/day concurrently for 3 days. BREYANZI was administered in the inpatient (88%) and outpatient (12%) settings.

Of 113 patients who underwent leukapheresis, 94 received BREYANZI. Of the 94, 84 received BREYANZI at 90 to 111 × 10^6 CAR-positive T cells and 10 received a cell-dose outside of this dose range; 3 received CAR-positive T cells that did not meet the product specifications for BREYANZI (manufacturing failure); and 16 other patients did not receive BREYANZI for other reasons.

The median time from leukapheresis to product availability was 24 days (range: 19 to 84 days), and the median time from leukapheresis to product infusion was 36 days (range: 28 to 384 days). Of the 89 patients treated with BREYANZI, 69 (78%) received bridging therapy.

Patients had measurable disease present before BREYANZI administration based on IRC assessment. Nineteen of 84 patients were not evaluable for efficacy (13 patients did not have baseline disease assessments performed after completion of bridging therapy, 1 patient lacked measurable disease, and 5 had Richter’s transformation). Of the 65 efficacy-evaluable patients, the median age was 66 years (range: 49 to 82 years), 68% were male, 80% were White, 3% were Black, 1% were Asian. Two-percent were Hispanic and 89% were non-Hispanic. Eighty-three percent of patients had at least one high risk genetic attribute including 43% del(17p), 45% TP53 mutation, 45% unmutated IGHV, and 62% with complex karyotype. Fifty-one percent of the patients had bulky disease. The median number of prior therapies was 5 (range: 2 to 12). All 65 patients were exposed to a BTK inhibitor, of which 88% were refractory, 1.5% were relapsed, and 11% were intolerant. Of 65 patients who received a BCL-2 inhibitor, 92% were refractory, none relapsed, and 6% were intolerant. A total of 83% had disease refractory to last therapy.

Efficacy was based on ORR (including CR and PR) and DOR as determined by an IRC using 2018 International Workshop CLL (iwCLL) criteria (Tables 23 and 24). The median time to first response (CR or PR) was 1.1 months (range: 0.8 to 17.4 months). The median time to first CR was 3.0 months (range 1.1 to 17.9 months).

Table 23: Response Rate in Relapsed or Refractory CLL/SLL (Study 4)
Outcome | BREYANZI Treated; (N=65) | All Leukapheresed; (N=113)
Overall Response Ratea, n (%) | 29 (45) | 42 (37)
[95% CI]b | [32.3, 57.5] | [28.3, 46.8]
Complete Responsea, n (%) | 13 (20) | 16 (14)
[95% CI]b | [11.1, 31.8] | [8.3, 22.0]
Partial Responsea, n (%) | 16 (25) | 26 (23)
[95% CI]b | [14.8, 36.9] | [15.6, 31.9]
CI=confidence interval; iwCLL=international workshop on chronic lymphocytic leukemia; IRC=independent review committee.
a Per the 2018 iwCLL criteria, as assessed by IRC.
b 2-sided 95% exact Clopper-Pearson CIs.

Table 24: Duration of Response in Study 4
 | BREYANZI-Treated; N=65
Number of Responders | 29
DORa (months)
Median [95% CI]b | 35.3 [12.4, NR]
Range | 2.0^+, 35.3
DOR if Best Response is CRa (months) | N=13
Median [95% CI]b | NR [15.0, NR]
Range | 2.0^+, 30.0^+
Rate at 12 months (%) [95% CI]b | 100 [NR, NR]
Rate at 18 months (%) [95% CI]b | 87.5 [38.7, 98.1]
DOR if Best response is PRa (months) | N=16
Median [95% CI]b | 12.4 [8.9, NR]
Range | 4.1, 35.3
Rate at 12 months (%) [95% CI]b | 60.3 [32.0, 79.8]
Rate at 18 months (%) [95% CI]b | 46.9 [21.4, 68.9]
CI=confidence interval; NR=not reached.
a Per the 2018 iwCLL criteria, as assessed by IRC.
b Kaplan-Meier method was used to obtain 2-sided 95% CIs.
^+ Indicates a censored value.

Minimal residual disease (MRD) negative status was defined as less than one CLL cell per 10^4 leukocytes using ClonoSEQ, a next generation sequencing assay (NGS) at any time post infusion (MRD‑negativity rate). There was no statistical testing of MRD-negativity rate. In patients who achieved CR, the MRD-negativity rate was 100% (13/13, 95% CI: 75.3, 100) in peripheral blood and 92.3% (12/13, 95% CI: 64, 99.8) in the bone marrow.

14.3 Relapsed or Refractory Follicular Lymphoma

The efficacy of BREYANZI was evaluated in a Phase 2, open-label, multicenter, single-arm trial (Study 5 ‑ FL Cohort: JCAR017-FOL-001; NCT04245839) in adult patients with relapsed or refractory FL after two or more lines of systemic therapy (including an anti-CD20 antibody and an alkylating agent). The study enrolled patients with ECOG performance status of ≤ 1. The study excluded patients with a creatinine clearance of ≤ 30 mL/min, ALT > 5 times the ULN, or LVEF < 40%. There was no prespecified threshold for blood counts; patients were eligible to enroll if they were assessed by the investigator to have adequate bone marrow function to receive lymphodepleting chemotherapy. The planned dose of BREYANZI was 100 × 10^6 CAR-positive viable T cells. Bridging therapy for disease control was permitted between apheresis and the start of lymphodepleting chemotherapy.

A single dose of BREYANZI was administered 2 to 7 days following completion of lymphodepleting chemotherapy. The lymphodepleting chemotherapy regimen consisted of fludarabine 30 mg/m^2/day and cyclophosphamide 300 mg/m^2/day concurrently for 3 days. Six percent of patients were treated with BREYANZI in outpatient setting.

Of 114 patients who underwent leukapheresis, 107 received BREYANZI and the median dose administered was 100.02 x 10^6 CAR-positive viable T-cells (range: 93.4 to 109.2 x 10^6 CAR-positive viable T cells).The primary efficacy analysis included 94 patients who had PET-positive disease at study baseline or confirmation of PET-positive disease after bridging therapy, received conforming product in intended dose range and had at least 9 months of follow up from the date of first response.

The median time from leukapheresis to product availability was 29 days (range: 20 to 55 days), and the median time from leukapheresis to product infusion was 50 days (range: 31 to 313 days). Of the 107 patients treated with BREYANZI, 40 (40%) received bridging therapy.

The median age was 63 years (range: 23 to 80 years), 62% were male, ECOG performance status was 0 in 63% and 1 in 37% of patients; 55% were White, 3% were Black, 9% were Asian; 5% were Hispanic and 69% were non-Hispanic. The median number of prior systemic therapies was 3 (range: 2 to 10), with 46% receiving 2 prior lines, 22% receiving 3 prior lines and 32% receiving ≥ 4 prior lines. Twenty percent had received rituximab with lenalidomide, 25% had received a PI3K inhibitor, and 29% of patients had prior autologous HSCT. Eighty-nine percentage patients had Stage III-IV disease at study entry, 29% had bulky disease, 64% had progression within 6 months of the most recent regimen, and 50% had progression within 24 months of initial diagnosis (POD24).

Efficacy was based on ORR, defined as the percentage of patients with a best overall response (BOR) of CR or PR after BREYANZI infusion and duration of response as determined by an IRC (Tables 25 and 26). The median time to first response (CR or PR) was 1.0 month (range: 0.6 to 3.3 months). The median time to first CR was 3.0 months (range 0.6 to 18.0 months).

Table 25: Response Rate in Patients with Relapsed or Refractory FL
 | BREYANZI‑Treateda; (N=94) | All Leukapheresed; (N=114)
Overall Response Rateb, n (%) | 90 (95.7) | 105 (92.1)
[95% CI]c | [89.5, 98.8) | [85.5, 96.3]
Complete Responsed, n (%) | 69 (73.4) | 78 (68.4)
[95% CI] | [63.3, 82.0] | [59.1, 76.8)
Partial Response, n (%) | 21 (22.3) | 27 (23.7)
[95% CI] | [14.4, 32.1] | [16.2, 32.6]
CI=confidence interval.
a Evaluable for efficacy.
b Per the Lugano criteria, as assessed by an IRC.
c Two-sided 95% confidence interval based on exact Clopper-Pearson method.
d CR required a negative bone marrow biopsy after treatment in patients who did not have a negative bone marrow biopsy between their most recent disease progression and prior to initiation of lymphodepleting chemotherapy.

Table 26: Duration of Responsea in Patients with Relapsed or Refractory FL
 | BREYANZI Treatedb; N = 94
Number of Responders | 90
DOR (months)
Median [95% CI]c | NR (18.0, NR)
Range | 1.9, 23.1^+
Rate at 12 months, (%) [95% CI]d | 80.9 (71.0, 87.7)
Rate at 18 months, (%) [95% CI]d | 77.1 (65.9, 85.0)
DOR if best response is CR (months) | N=69
Median [95% CI]c | NR [NR, NR]
Range | 2.8, 23.1^+
Rate at 12 months, (%) [95% CI]d | 88.2 (77.7, 93.9)
Rate at 18 months, (%) [95% CI]d | 83.1 (70.0, 90.9)
DOR if best response is PR (months) | N=21
Median [95% CI]c | 18.04 [4.17, NR]
Range | 1.9, 22.4^+
Rate at 12 months, (%) [95% CI]d | 56.7 (33.3, 74.7)
Rate at 18 months, (%) [95% CI]d | 56.7 (33.3, 74.7)
DOR= duration of response; CI=confidence interval; CR=complete response; PR=partial response; NR=not reached.
a Median follow-up for DOR is 16.8 months (95% CI: 16.3 to 17.0).
b Evaluable for efficacy.
c Median [95% CI] are estimated from KM estimates.
d KM estimate of probability of continued response at the specified month.
^+ Indicates a censored value.

14.4 Relapsed or Refractory Mantle Cell Lymphoma

The efficacy of BREYANZI was evaluated in an open-label, multicenter, single-arm trial (Study 3 - MCL Cohort: 017001; NCT02631044) in adult patients with relapsed or refractory MCL who had received at least two prior lines of therapy including a BTK inhibitor, an alkylating agent, and an anti-CD20 agent. The study included patients with ECOG performance status of ≤ 1, prior autologous and/or allogeneic HSCT, and secondary CNS lymphoma involvement. The study excluded patients with a creatinine clearance ≤ 30 mL/min, alanine aminotransferase > 5 times the upper limit of normal or left ventricular ejection fraction (LVEF) < 40%. There was no prespecified threshold for blood counts; patients were eligible to enroll if they were assessed by the investigator to have adequate bone marrow function to receive lymphodepleting chemotherapy. The planned dose of BREYANZI was 100 × 10^6 CAR-positive viable T cells. Bridging therapy for disease control was permitted between apheresis and the start of lymphodepleting chemotherapy.

BREYANZI was administered 2 to 7 days following completion of lymphodepleting chemotherapy. The lymphodepleting chemotherapy regimen consisted of fludarabine 30 mg/m^2/day and cyclophosphamide 300 mg/m^2/day concurrently for 3 days. BREYANZI was administered in the inpatient (85%) and outpatient (15%) setting.

Of 89 patients who underwent leukapheresis, 71 received BREYANZI and the median dose administered was 99.8 x 10^6 CAR-positive viable T cells (range: 90 to 103 x 10^6 CAR-positive viable T cells). The primary efficacy analysis included a total of 68 patients with MCL who received at least 2 prior lines of therapy including a BTK inhibitor, had PET-positive disease at study baseline or after bridging therapy, received conforming product in the intended dose range, and had at least 6 months of follow up from the date of first response.

The median time from leukapheresis to product availability was 24 days (range: 17 to 80 days), and the median time from leukapheresis to product infusion was 36 days (range: 28 to 489 days). Of the 68 patients in the main efficacy population, 44 (65%) received bridging therapy.

The median age was 69 years (range: 36 to 86 years); 75% were male, ECOG performance status was 0 in 57% and 1 in 43% of patients; 87% were White, 1.5% were Black, 6% were Asian; 6% were Hispanic and 91% were non-Hispanic. The median number of prior therapies was 3 (range: 2 to 11) and 32% had received prior HSCT. Twenty-nine percent of patients had blastoid morphology and 10% had CNS lymphoma involvement at baseline. Sixty-nine percent of patients had disease refractory to their last therapy for MCL, defined as best response of partial response (PR), stable disease (SD), or progressive disease (PD) to last systemic or HSCT treatment with curative intent. All 68 patients were exposed to BTK inhibitor, of which 56% were refractory, defined as any response to prior BTK inhibitor that was less than PR.

Efficacy was based on ORR, defined as the percentage of patients with BOR of either CR or PR after BREYANZI infusion, as determined by an IRC using 2014 Lugano classification. Other efficacy measures included complete response rate and DOR, as determined by IRC (Tables 27 and Table 28).

Both the median time to first response (CR or PR) and the median time to first CR were 1 month (range: 0.7 to 3 months).

Table 27: Response Rate in Relapsed or Refractory MCL (Study 3 - MCL Cohort)
Outcome | BREYANZI-Treateda; (N=68) | All Leukapheresed; (N=89)
Overall Response Rateb, n (%); [95% CI]c | 58 (85.3); (74.6, 92.7) | 65 (73.0); (62.6, 81.9)
Complete Response, n (%); [95% CI] | 46 (67.6); (55.2, 78.5) | 51 (57.3); (46.4, 67.7)
Partial Response, n (%); [95% CI] | 12 (17.6); (9.5, 28.8) | 14 (15.7); (8.9, 25.0)
CI=confidence interval.
a Evaluable for efficacy.
b Per the 2014 Lugano classification (including bone marrow biopsy assessments), as assessed by IRC.
c 2-sided 95% exact Clopper-Pearson CIs.

Table 28: Duration of Responsea in Study 3 - MCL Cohort
 | BREYANZI-Treated; (N=68)
Number of Responders | 58
DORb (months); Median [95% CI]c; Range | 13.3 [6.0, 23.3]; 0.0^+, 23.3^+
Rate at 12 months (%) [95% CI]d | 51.4 [37.5, 63.7]
Rate at 18 months (%) [95% CI]d | 38.8 [25.0, 52.4]
DOR if Best Response is CRb (months); Median [95% CI]c; Range | N=46; 17.5 [7.5, NR]; 0.6, 23.3^+
Rate at 12 months (%) [95% CI]d | 57.8 [41.9, 70.7]
Rate at 18 months (%) [95% CI]d | 48.0 [31.6, 62.6]
DOR if Best Response is PRb (months); Median [95% CI]c; Range | N=12; 2.2 [1.8, 13.3]; 0.0^+, 14.5
Rate at 12 months (%) [95% CI]d | 27.3 [6.5, 53.9]
Rate at 18 months (%) [95% CI]d | 0.0 [NE, NE]
CI=confidence interval; NE=not evaluable; NR=not reached.
a Median follow-up for DOR is 22.2 months (95% CI: 16.7 to 22.8).
b Per the 2014 Lugano classification (including bone marrow biopsy assessments), as assessed by IRC.
c Kaplan-Meier method was used to obtain 2-sided 95% CIs.
d KM estimate of probability of continued response at the specified month.
^+ Indicates a censored value.

14.5 Relapsed or Refractory Marginal Zone Lymphoma

The efficacy of BREYANZI was evaluated in an open-label, multicenter, single-arm study (Study 5 – MZL Cohort: JCAR017-FOL-001; NCT04245839) in adult patients with relapsed or refractory MZL. The study enrolled patients who had received at least two or more lines of systemic therapy (including an anti-CD20 antibody and an alkylating agent) or who relapsed after hematopoietic stem cell transplant (HSCT). Confirmation of the presence of CD19-positive lymphoma on biopsy was required for patients with prior CD19-directed therapy. The indication for systemic treatment was based on investigator’s assessment. The study included patients with ECOG performance status of ≤ 1 and excluded patients with a creatinine clearance of ≤ 30 mL/min, ALT > 5 times the ULN, or LVEF < 40%. The study also excluded patients with transformed lymphoma, active or serious infections, active autoimmune disease requiring immunosuppressive therapy, or a history of a central nervous system disorder. There was no prespecified threshold for blood counts; patients were eligible to enroll if they were assessed by the investigator to have adequate bone marrow function to receive lymphodepleting chemotherapy.

The planned dose of BREYANZI was 100 × 10^6 CAR-positive viable T cells. Bridging therapy for disease control was permitted between apheresis and the start of lymphodepleting chemotherapy.

A single dose of BREYANZI was administered 2 to 7 days following completion of lymphodepleting chemotherapy. The lymphodepleting chemotherapy regimen consisted of fludarabine 30 mg/m^2/day and cyclophosphamide 300 mg/m^2/day concurrently for 3 days. BREYANZI was administered in the inpatient (79%) and outpatient (21%) setting.

Of 77 patients who underwent leukapheresis, 69 received lymphodepleting chemotherapy, 67 received BREYANZI and 2 patients received nonconforming product. Thirty-four (44%) of the 77 leukapheresed patients received bridging therapy. The most commonly used agents (>= 5%) included: anti-CD20 directed therapy (26%), steroids (17%), alkylating agents (18%), vincristine (9%), platinum chemotherapy (7%), Bruton tyrosine kinase inhibitors (10%), anthracycline (8%), and gemcitabine (5%). Eight patients did not receive lymphodepleting chemotherapy following leukapheresis due to progressive disease in 4 patients, failure to meet treatment criteria in 3 patients, and suicide in 1 patient.

The population demographics and disease characteristics of the 77 patients who were leukapheresed were as follows: median age was 64 years (range: 37 to 81 years), 61% were male, ECOG performance status was 0 in 53% and 1 in 47% of patients; 56% were White, 5% were Asian, 3% were Black; and 4% were Hispanic. Thirty-seven patients (48%) had nodal MZL, 19 (25%) patients had extranodal MZL/mucosa-associated lymphoid tissue (MALT), and 21 (27%) patients had splenic MZL. The median number of prior systemic therapies was 3 (range: 2 to 12), with 43% receiving 2 prior lines, 23% receiving 3 prior lines, and 34% receiving ≥ 4 prior lines. Seventy-nine percent had received bendamustine, 20% had received rituximab with lenalidomide, 9% had received prior zanubrutinib, and 14% of patients had prior autologous HSCT. Eighty-seven percent of patients had Stage III-IV disease at study entry, 23% had bulky disease, 35% had progression within 6 months of the most recent regimen, and 33% had progression within 24 months of initiation of first line chemoimmunotherapy with anti-CD20 and alkylating agent (POD24).

The median dose administered was 100.2 × 10^6 CAR-positive viable T-cells (range: 97.3 to 102.8 × 10^6 CAR-positive viable T cells). The primary efficacy analysis included 66 patients who had confirmed measurable disease by CT at study baseline or after bridging therapy and received conforming product in intended dose range and had at least 9 months of follow up from the date of first response.

The median time from leukapheresis to product availability was 29 days (range: 21 to 44 days), and the median time from leukapheresis to product infusion was 50 days (range: 30 to 121 days).

The main efficacy outcome measure was based on overall response rate (ORR), defined as the percentage of patients with the best overall response (BOR) of CR or PR after BREYANZI infusion, and duration of response as determined by an independent review committee (IRC). In the BREYANZI-treated patients, the median time to first response (CR or PR) was 0.95 months (range: 0.8 to 29.7 months). The median time to first CR was 5.55 months (range 0.9 to 29.7 months).

The efficacy results are summarized in Table 29 and Table 30 below.

Table 29: Response Rate in Patients with Relapsed or Refractory MZL
 | BREYANZI‑Treateda; (N=66) | All Leukapheresede; (N=77)
Overall Response Rateb, n (%); [95% CI]c | 63 (95.5) | 65 (84.4)
Overall Response Rateb, n (%); [95% CI]c | [87.3, 99.1] | [74.4, 91.7]
Complete Responsed, n (%); [95% CI] | 41 (62.1); [49.3, 73.8] | 43 (55.8); [44.1, 67.2]
Partial Response, n (%); [95% CI] | 22 (33.3); [22.2, 46.0] | 22 (28.6); [18.8, 40.0]
CI=confidence interval.
a Evaluable for efficacy.
b Per the Lugano criteria (based on CT only), as assessed by an IRC.
c Two-sided 95% confidence interval based on exact Clopper-Pearson method.
d CR required a negative bone marrow biopsy after treatment in patients who did not have a negative bone marrow biopsy between their most recent disease progression and prior to initiation of lymphodepleting chemotherapy.
e Leukapheresed patients includes patients who were leukapheresed but did not receive BREYANZI for the following reasons: Progressive disease (n=4); Failure to meet treatment criteria (n=3); Received nonconforming product (n=2); and Suicide (n=1).

Table 30: Duration of Responsea in Patients with Relapsed or Refractory MZL
 | BREYANZI-Treatedb; (N = 66)
Number of Responders | 63
DOR (months)
Median [95% CI]c | NR [25.59, NR]
Range | 0.0^+, 35.3^+
Rate at 12 months, (%) [95% CI]d | 96.7 (87.3, 99.2)
Rate at 24 months, (%) [95% CI]d | 90.1 (73.1, 96.6)
DOR if best response is CR (months) | N=41
Median [95% CI]c | NR [24.48, NR]
Range | 0.0^+, 35.3^+
Rate at 12 months, (%) [95% CI]d | 94.9 (81.2, 98.7)
Rate at 24 months, (%) [95% CI]d | 89.0 (66.6, 96.7)
DOR if best response is PR (months) | N=22
Median [95% CI]c | 25.59 [25.59, NR]
Range | 2.0^+, 32.8^+
Rate at 12 months, (%) [95% CI]d | 100 (100.0, 100.0)
Rate at 24 months, (%) [95% CI]d | 93.3 (61.3, 99.0)
DOR= duration of response; CI=confidence interval; CR=complete response; PR=partial response; NR=not reached.
a Median follow-up for DOR is 21.59 months (95% CI: 17.28 to 22.77) for treated set and 22.31 months (95% CI: 17.28, 22.97) for Leukapheresed Set.
b Evaluable for efficacy.
c Median [95% CI] are estimated from KM estimates.
^+ Indicates a censored value.
d KM estimate of probability of continued response at the specified month.

In subgroup analysis, overall response rate per IRC was 94.1% (95% CR: 71.3, 99.9) with a CR rate of 47.1% (95% CI: 23.0, 72.2) among 17 patients with extranodal marginal zone lymphoma; 96.9% (95% CI: 83.8, 99.9) with a CR rate of 62.5% (95% CI: 43.7, 78.9) among 32 patients with nodal marginal zone lymphoma; and 94.1% (95% CI 71.3, 99.9) with a CR rate of 76.5% (95% CI: 50.1, 93.2) among 17 patients with splenic marginal zone lymphoma.

15 REFERENCES

1. Lee DW, Gardner R, Porter DL, et al. Current concepts in the diagnosis and management of cytokine release syndrome. Blood 2014; 124:188-195.

16 HOW SUPPLIED/STORAGE AND HANDLING

BREYANZI consists of genetically modified autologous T cells, supplied in vials as separate frozen suspensions of each CD8 component (NDC 73153-901-08) and CD4 component (NDC 73153-902-04). Each CD8 or CD4 component is packed in a carton containing up to 4 vials, depending upon the concentration of the cryopreserved drug product CAR-positive viable T cells. The cartons for each CD8 component and CD4 component are in an outer carton (NDC 73153-900-01). BREYANZI is shipped directly to the cell lab or clinical pharmacy associated with the infusion center in the vapor phase of a liquid nitrogen shipper. A Release for Infusion (RFI) Certificate for each component and patient-specific syringe labels are affixed inside the shipper.

- Confirm patient identity upon receipt.
- Store vials in the vapor phase of liquid nitrogen (less than or equal to minus 130°C) in a temperature-monitored system.
- Thaw BREYANZI prior to infusion [see Dosage and Administration (2.2)].

17 PATIENT COUNSELING INFORMATION

Advise the patient to read the FDA-approved patient labeling (Medication Guide).

Ensure that patients understand the risk (11%) of manufacturing failure. In case of a manufacturing failure, a second manufacturing of BREYANZI may be attempted. While the patient awaits the product, additional bridging therapy (not the lymphodepletion) may be necessary. This bridging therapy may be associated with adverse events during the pre-infusion period, which could delay or prevent the administration of BREYANZI.

Advise patients that they will be monitored daily for at least 7 days following the BREYANZI infusion and instruct patients to remain close to a healthcare facility for at least 2 weeks following the infusion.

Prior to infusion, advise patients of the following risks:

- Cytokine Release Syndrome (CRS) – Signs and symptoms of CRS (fever, chills, hypotension, tachycardia, hypoxia, and fatigue). Counsel patients to seek immediate medical attention should signs or symptoms of CRS occur at any time [see Warnings and Precautions (5.1) and Adverse Reactions (6.1)].
- Neurologic Toxicities – Signs or symptoms associated with neurologic events including encephalopathy, confusion, decreased consciousness, speech disorders, tremor, and seizures. Counsel patients to seek immediate medical attention should signs or symptoms of neurologic toxicity occur at any time [see Warnings and Precautions (5.2) and Adverse Reactions (6.1)].
- Serious Infections – Signs or symptoms associated with infection [see Warnings and Precautions (5.4) and Adverse Reactions (6.1)].
- Prolonged Cytopenias – Signs or symptoms associated with bone marrow suppression including neutropenia, anemia, thrombocytopenia, or febrile neutropenia [see Warnings and Precautions (5.5) and Adverse Reactions (6.1)].
- Secondary Malignancies: Secondary malignancies, including T cell malignancies, have occurred [see Boxed Warning, Warnings and Precautions (5.7), Adverse Reactions (6.2)].

Advise patients of the need to:

- Contact Bristol-Myers Squibb at 1-888-805-4555 if they are diagnosed with a secondary malignancy [see Warnings and Precautions (5.7)].
- Avoid driving for at least 2 weeks after BREYANZI administration.

Manufactured by:

Juno Therapeutics Inc., a Bristol-Myers Squibb Company, Bothell, WA 98021. US License No.: 2156.

Celgene Corporation, a Bristol-Myers Squibb Company, Summit, NJ 07901. US License No.: 2252.

Bristol-Myers Squibb Company, Devens, MA 01434. US License No.: 1713.

BREYANZI® is a trademark of Juno Therapeutics, Inc., a Bristol-Myers Squibb Company.

Pat. https://www.bms.com/patient-and-caregivers/our-medicines.html

BREPI.010/MG.009

MEDICATION GUIDE
BREYANZI® (pronounced braye an' zee)
(lisocabtagene maraleucel)

Read this Medication Guide before you start your BREYANZI treatment. The more you know about your treatment, the more active you can be in your care. Talk with your healthcare provider if you have questions about your health condition or treatment. Reading this Medication Guide does not take the place of talking with your healthcare provider about your treatment.

What is the most important information I should know about BREYANZI?
BREYANZI may cause side effects that are life-threatening and can lead to death. Call your healthcare provider or get emergency help right away if you get any of the following:

- difficulty breathing
- fever (100.4°F/38°C or higher)
- chills/shaking chills
- confusion
- severe nausea, vomiting, diarrhea
- fast or irregular heartbeat
- dizziness/lightheadedness
- severe fatigue or weakness

It is important that you tell your healthcare providers that you have received BREYANZI and to show them your BREYANZI Patient Wallet Card. Your healthcare provider may give you other medicines to treat your side effects.

What is BREYANZI?
BREYANZI is a prescription medicine used to treat five types of non-Hodgkin lymphoma:

- Large B cell lymphoma, when:
  - your first treatment has not worked or your cancer returned within a year of your first treatment OR
  - your first treatment has not worked or your cancer returned after the first treatment, and you are not eligible for hematopoietic stem cell transplantation because of medical conditions or age OR
  - two or more kinds of treatment have not worked or stopped working.
- Chronic lymphocytic leukemia or small lymphocytic lymphoma when two or more kinds of treatment have not worked or stopped working.
- Follicular lymphoma, when two or more kinds of treatment have not worked or stopped working.
- Mantle cell lymphoma when two or more kinds of treatment have not worked or stopped working, including a prior Bruton tyrosine kinase (BTK) inhibitor medicine.
- Marginal zone lymphoma when two or more kinds of treatment have not worked or stopped working.

BREYANZI is different than other cancer medicines because it is made from your own white blood cells, which have been genetically modified to recognize and attack your lymphoma cells.

Before getting BREYANZI, tell your healthcare provider about all your medical problems, including if you have or have had:

- Neurologic problems (such as seizures, stroke, or memory loss)
- Lung or breathing problems
- Heart problems
- Liver problems
- Kidney problems
- A recent or active infection

Tell your healthcare provider about all the medications you take, including prescription and over-the-counter medicines, vitamins, and herbal supplements.

How will I receive BREYANZI?

- BREYANZI is made from your own white blood cells, so your blood will be collected by a process called “leukapheresis” (LOO-kuh-feh-REE-sis).
- It takes about 3-4 weeks from the time your cells are received at the manufacturing site and are available to be shipped back to your healthcare provider, but the time may vary.
- Before you get BREYANZI, you will get 3 days of chemotherapy to prepare your body.
- When your BREYANZI is ready, your healthcare provider will give it to you through a catheter (tube) placed into your vein (intravenous infusion). BREYANZI is given as infusions of 2 different cell types.
  - You will receive infusions of one cell type, immediately followed by the other cell type.
  - The time for infusion will vary but will usually be less than 15 minutes for each of the 2 cell types.
- During the first week, you will be monitored daily.
- You should plan to stay close to a healthcare facility for at least 2 weeks after getting BREYANZI. Your healthcare provider will check to see that your treatment is working and help you with any side effects that may occur.
- You may be hospitalized for side effects and your healthcare provider will discharge you if your side effects are under control, and it is safe for you to leave the hospital.
- Your healthcare provider will want to do blood tests to follow your progress. It is important that you do have your blood tested. If you miss an appointment, call your healthcare provider as soon as possible to reschedule.

What should I avoid after receiving BREYANZI?

- Avoid driving for at least 2 weeks after you get BREYANZI.
- Do not donate blood, organs, tissues, or cells for transplantation.

What are the possible or reasonably likely side effects of BREYANZI?

The most common side effects of BREYANZI are:

- fatigue
- difficulty breathing
- fever (100.4°F/38°C or higher)
- chills/shaking chills
- confusion
- difficulty speaking or slurred speech
- severe nausea, vomiting, diarrhea
- headache
- dizziness/lightheadedness
- fast or irregular heartbeat
- swelling
- low blood pressure
- muscle pain

BREYANZI can increase the risk of life-threatening infections that may lead to death. Tell your healthcare provider right away if you develop fever, chills, or any signs or symptoms of an infection.
BREYANZI can lower one or more types of your blood cells (red blood cells, white blood cells, or platelets). After treatment, your healthcare provider will test your blood to check for this. Tell your healthcare provider right away if you get a fever, are feeling tired, or have bruising or bleeding.

BREYANZI may increase your risk of getting cancers including certain types of blood cancers. Your healthcare provider should monitor you for this.
Having BREYANZI in your blood may cause a false-positive HIV test result by some commercial tests.
These are not all the possible side effects of BREYANZI. Call your doctor for medical advice about side effects. You may report side effects to FDA at 1-800-FDA-1088.

General information about the safe and effective use of BREYANZI
Medicines are sometimes prescribed for purposes other than those listed in a Medication Guide. If you would like more information about BREYANZI, talk with your healthcare provider. You can ask your healthcare provider for information about BREYANZI that is written for health professionals.
For more information, go to BREYANZI.com or call 1-888-805-4555.
Manufactured by:

Juno Therapeutics Inc., a Bristol-Myers Squibb Company, Bothell, WA 98021. US License No.: 2156.

Celgene Corporation, a Bristol-Myers Squibb Company, Summit, NJ 07901. US License No.: 2252.

Bristol-Myers Squibb Company, Devens, MA 01434. US License No.: 1713.
BREYANZI® is a trademark of Juno Therapeutics, Inc., a Bristol-Myers Squibb Company.
Pat. https://www.bms.com/patient-and-caregivers/our-medicines.html
BREMG.009 12/2025

This Medication Guide has been approved by the U.S. Food and Drug Administration. Revised: December 2025

PRINCIPAL DISPLAY PANEL - Kit Carton

lisocabtagene maraleucel
Breyanzi™

lisocabtagene maraleucel
Breyanzi®

NDC 73153-900-01
Rx only

FOR AUTOLOGOUS & INTRAVENOUS USE ONLY

Dispense with Medication Guide

Dosage: See Release for Infusion Certificate (inside shipper).

Contains DMSO 7.5% v/v.

1 to 4 single-dose vials/component. Each vial
contains up to 70 x 10^6 CAR-positive viable T cells/mL.
4.6 mL per vial.

Store at ≤ -130°C; vapor phase of liquid nitrogen.
Do not filter or irradiate.
Not evaluated for infectious substances.
Discard unused portion.

Manufactured by:
Juno Therapeutics, Inc., a Bristol-Myers Squibb Company
Bothell, WA 98021
Phone: 1-888-805-4555
US License #: 2156

304029

NDC 73153-900-01

VERIFY
PATIENT
ID

First: FIRST NAME
Last: LAST NAME
Date of birth: DD-MMM-YYYY
JOIN: XXXX-XXXXX
Aph ID/DIN: XXX XXX XXX XXX

CD8
component

CD4
component

Lot
XXXX-XXXXXY
XXXX-XXXXXY

Expiration
DD-MMM-YYYY
DD-MMM-YYYY

STOP
Confirm patient ID
prior to infusion